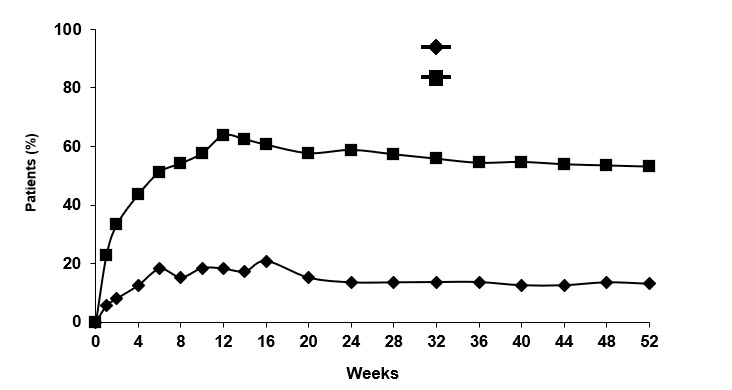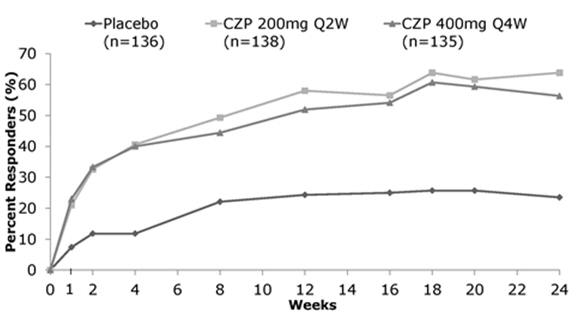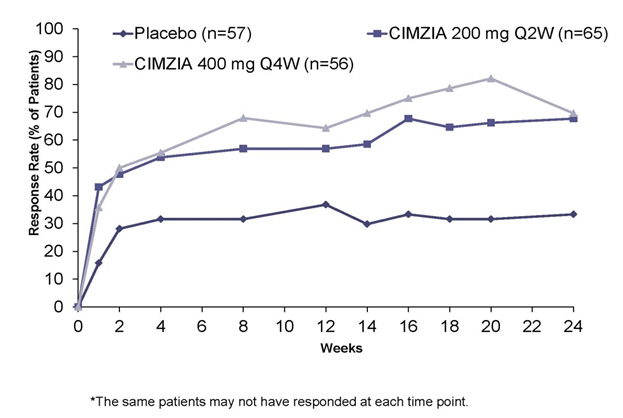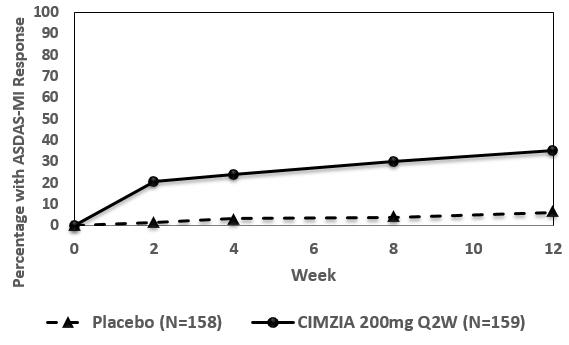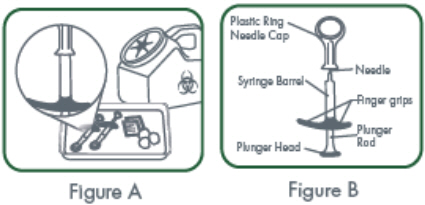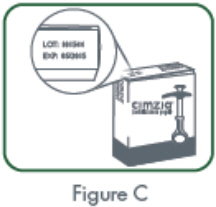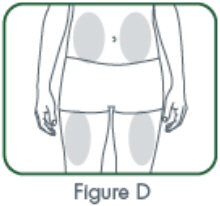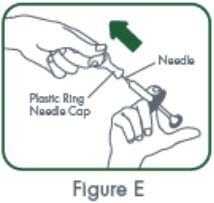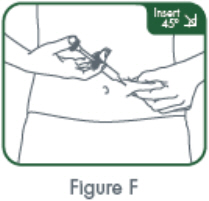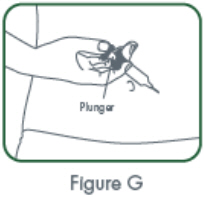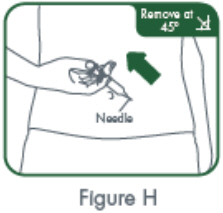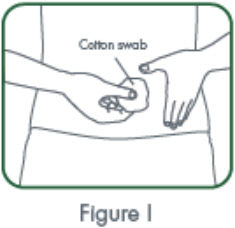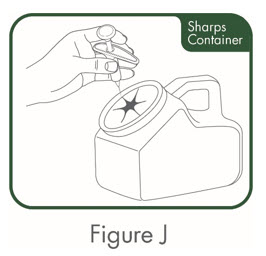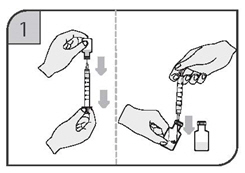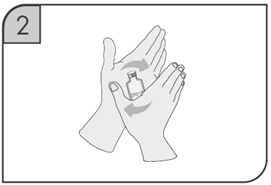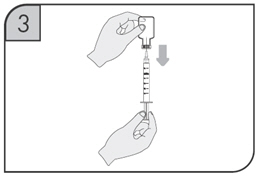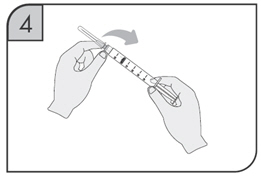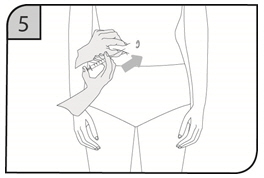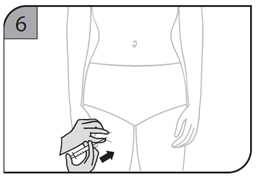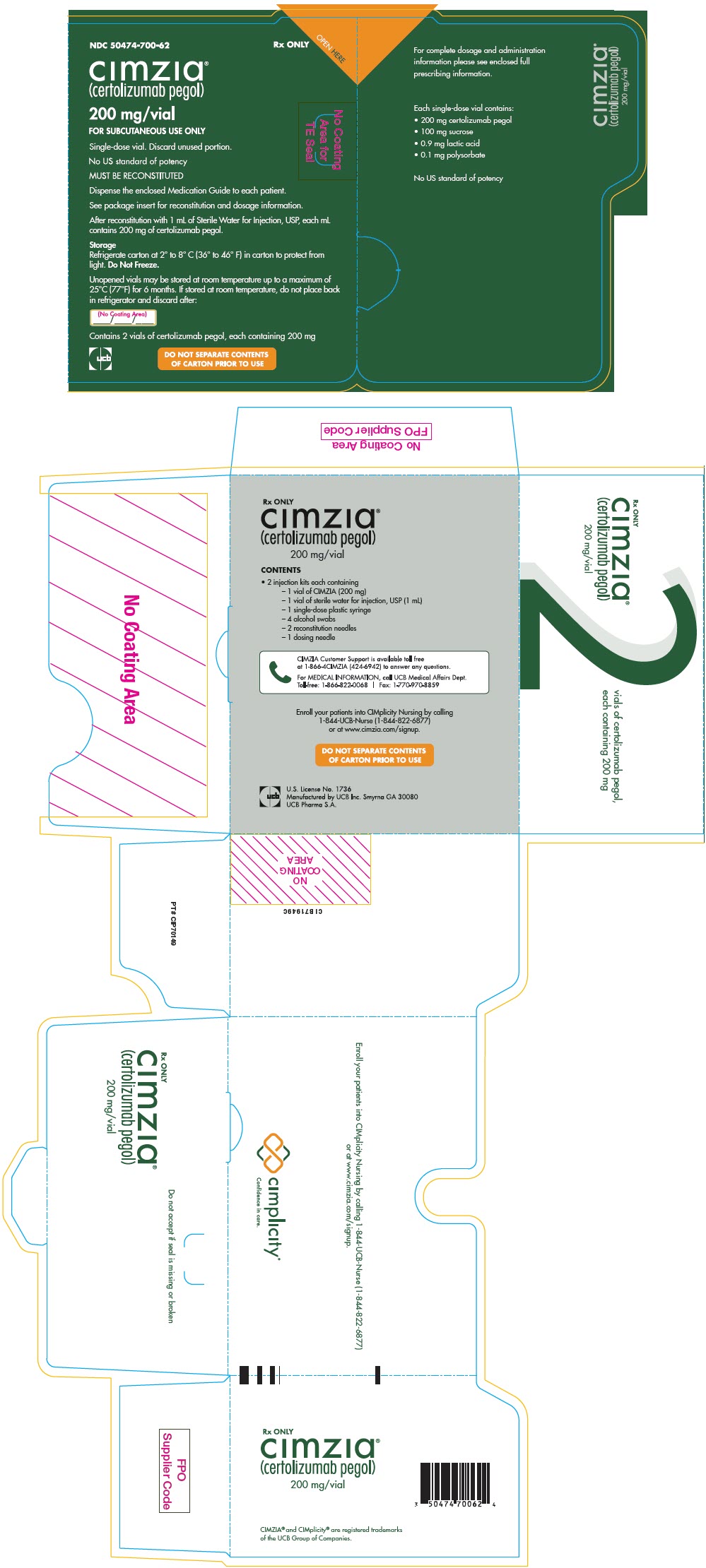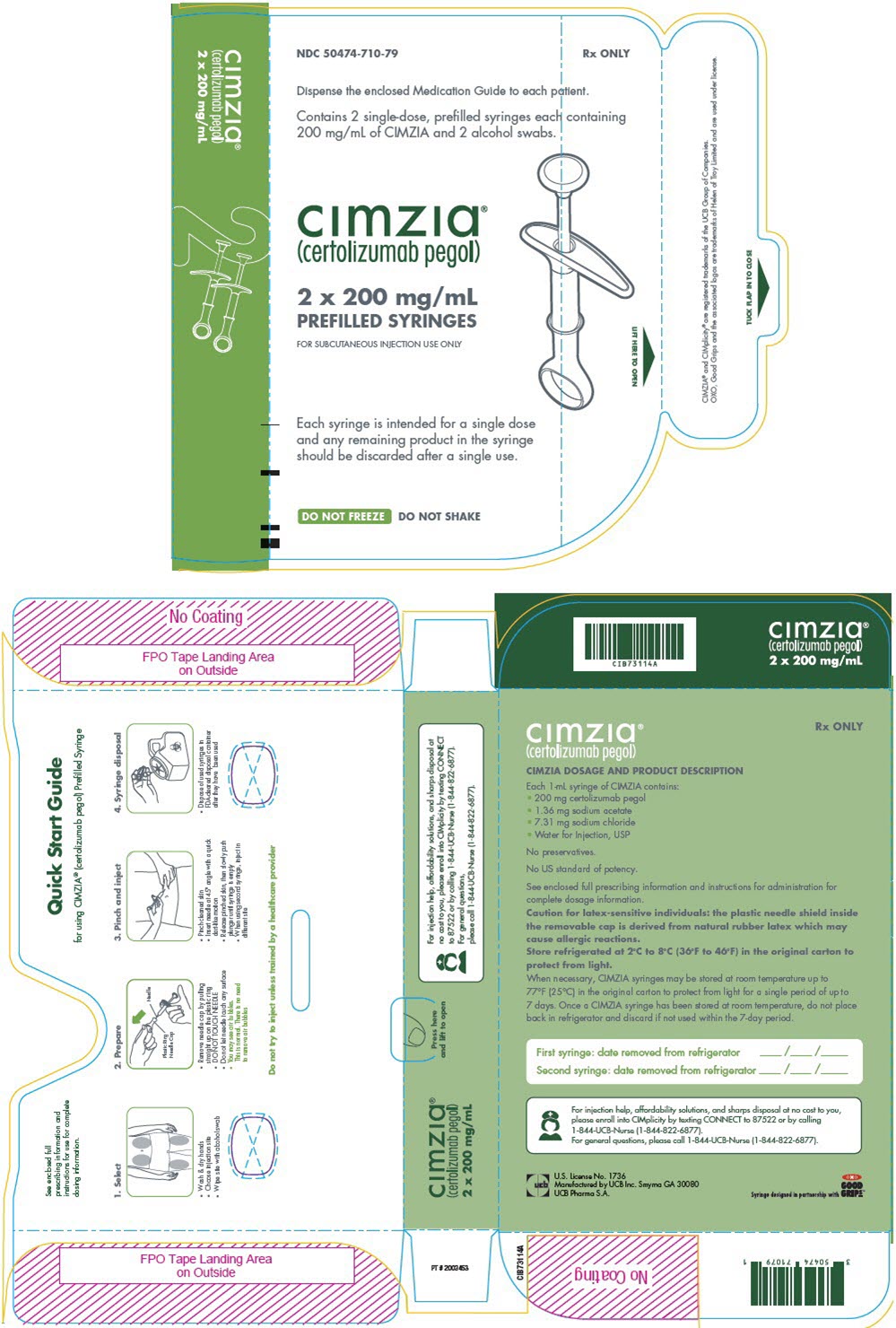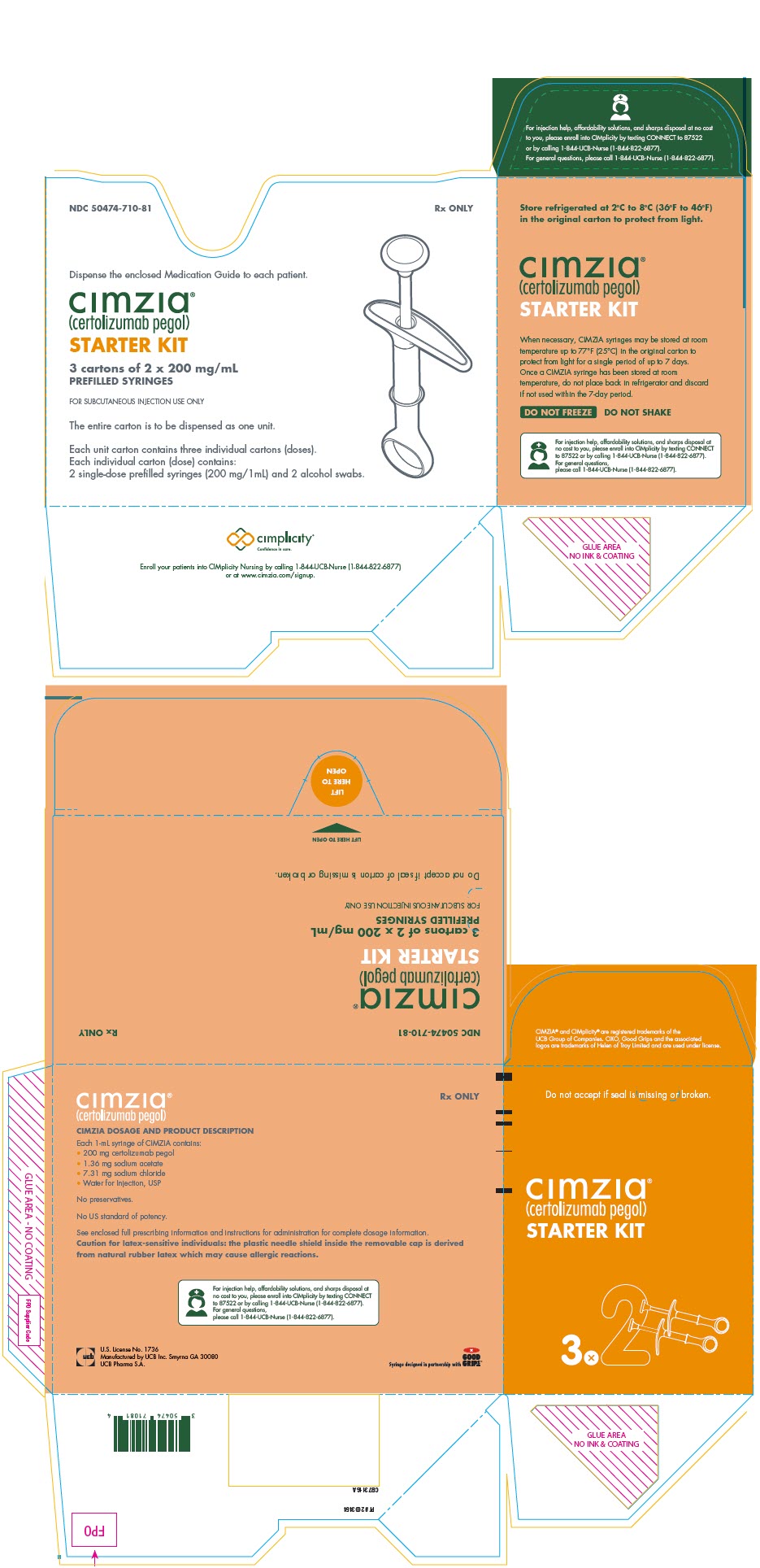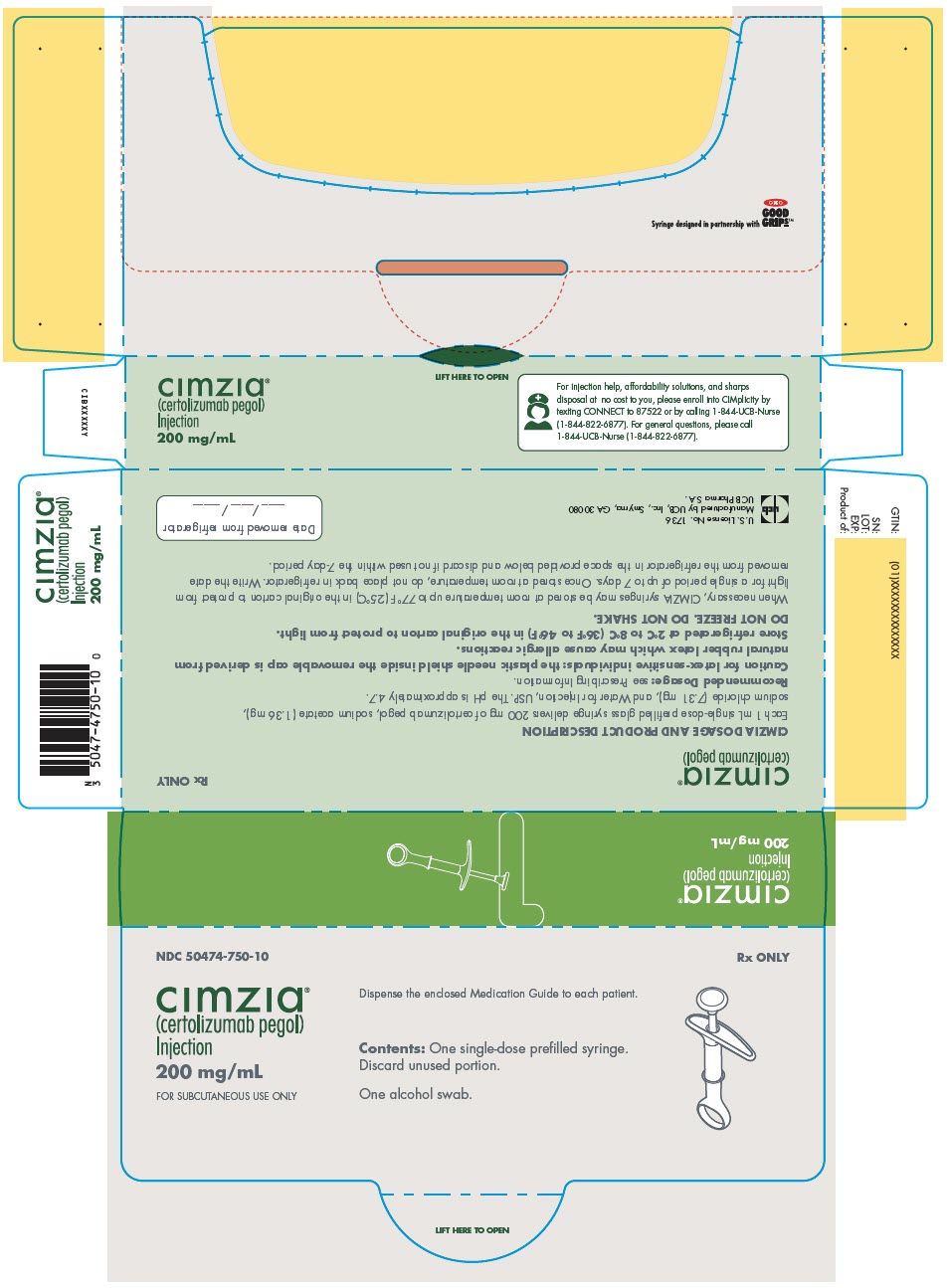 DRUG LABEL: Cimzia
NDC: 50474-700 | Form: KIT | Route: SUBCUTANEOUS
Manufacturer: UCB, Inc.
Category: prescription | Type: HUMAN PRESCRIPTION DRUG LABEL
Date: 20260224

ACTIVE INGREDIENTS: CERTOLIZUMAB PEGOL 200 mg/1 mL
INACTIVE INGREDIENTS: SUCROSE 100 mg/1 mL; LACTIC ACID, UNSPECIFIED FORM 0.9 mg/1 mL; WATER

HIGHLIGHTS OF PRESCRIBING INFORMATION

These highlights do not include all the information needed to use CIMZIA® safely and effectively. See full prescribing information for CIMZIA.
CIMZIA (certolizumab pegol) for injection, for subcutaneous use
CIMZIA (certolizumab pegol) injection, for subcutaneous use
Initial U.S. Approval: 2008

WARNING: SERIOUS INFECTIONS and MALIGNANCY

See full prescribing information for complete boxed warning.

- Increased risk of serious infections leading to hospitalization or death including tuberculosis (TB), bacterial sepsis, invasive fungal infections (such as histoplasmosis), and infections due to other opportunistic pathogens (5.1).
- CIMZIA should be discontinued if a patient develops a serious infection or sepsis (5.1).
- Perform test for latent TB; if positive, start treatment for TB prior to starting CIMZIA (5.1).
- Monitor all patients for active TB during treatment, even if initial latent TB test is negative (5.1)
- Lymphoma and other malignancies, some fatal, have been reported in children and adolescent patients treated with TNF blockers, of which CIMZIA is a member (5.2).

1 INDICATIONS AND USAGE

CIMZIA is a tumor necrosis factor (TNF) blocker indicated for:

- Reducing signs and symptoms of Crohn's disease and maintaining clinical response in adult patients with moderately to severely active disease who have had an inadequate response to conventional therapy (1.1)
- Treatment of adults with moderately to severely active rheumatoid arthritis (1.2)
- Treatment of active polyarticular juvenile idiopathic arthritis (pJIA) in patients 2 years of age and older (1.3)
- Treatment of adult patients with active psoriatic arthritis. (1.4)
- Treatment of adults with active ankylosing spondylitis (1.5)
- Treatment of adults with active non-radiographic axial spondyloarthritis with objective signs of inflammation (1.6)

Treatment of adults with moderate-to-severe plaque psoriasis who are candidates for systemic therapy or phototherapy (1.7)

2 DOSAGE AND ADMINISTRATION

CIMZIA is administered by subcutaneous injection (2).

Crohn's Disease (2.1)

- 400 mg initially and at Weeks 2 and 4. If response occurs, follow with 400 mg every four weeks

Rheumatoid Arthritis (2.2)

- 400 mg initially and at Weeks 2 and 4, followed by 200 mg every other week; for maintenance dosing, 400 mg every 4 weeks can be considered

Polyarticular Juvenile Idiopathic Arthritis (2.3)

- 10 kg (22 lbs) to less than 20 kg (44 lbs): 100 mg initially and at Weeks 2 and 4, followed by 50 mg every other week
- 20 kg (44 lbs) to less than 40 kg (88 lbs): 200 mg initially and at Weeks 2 and 4, followed by 100 mg every other week
- Greater than or equal to 40 kg (88 lbs): 400 mg initially and at Weeks 2 and 4, followed by 200 mg every other week

Psoriatic Arthritis (2.4)

- 400 mg initially and at week 2 and 4, followed by 200 mg every other week; for maintenance dosing, 400 mg every 4 weeks can be considered.

Ankylosing Spondylitis (2.5)

- 400 mg (given as 2 subcutaneous injections of 200 mg each) initially and at weeks 2 and 4, followed by 200 mg every other week or 400 mg every 4 weeks.

Non-radiographic Axial Spondyloarthritis (2.6)

- 400 mg (given as 2 subcutaneous injections of 200 mg each) initially and at weeks 2 and 4, followed by 200 mg every other week or 400 mg every 4 weeks.

Plaque Psoriasis (2.7,14.7)

- 400 mg (given as 2 subcutaneous injections of 200 mg each) every other week. For some patients (with body weight less than or equal to 90 kg), a dose of 400 mg (given as 2 subcutaneous injections of 200 mg each) initially and at Weeks 2 and 4, followed by 200 mg every other week may be considered.

3 DOSAGE FORMS AND STRENGTHS

- For injection: 200 mg lyophilized powder in a single-dose vial (3)
- Injection: 200 mg/mL solution in a single-dose prefilled syringe (3)

4 CONTRAINDICATIONS

Serious hypersensitivity reaction to certolizumab pegol or to any of the excipients. (4)

5 WARNINGS AND PRECAUTIONS

- Serious Infections: CIMZIA should not be initiated in patients with an active infection. Monitor for infection during and after treatment; discontinue if a serious infection develops. If invasive fungal infection develops in patients who reside or travel to regions where mycoses are endemic, consider empiric antifungal therapy. (5.1)
- Malignancies: Cases of lymphoma and other malignancies have been observed among patients receiving TNF blockers, including CIMZIA. (5.2)
- Heart Failure: Monitor patients for new onset or worsening congestive heart failure. (5.3)
- Hypersensitivity Reactions: Discontinue CIMZIA and institute appropriate therapy if anaphylaxis or other serious hypersensitivity reactions occur. (5.4)
- Hepatitis B Virus Reactivation: Test for HBV infection before starting CIMZIA. Monitor HBV carriers during and several months after therapy. If reactivation occurs, stop CIMZIA and begin anti-viral therapy (5.5)
- Neurologic Reactions: Exacerbation or new onset demyelinating disease may occur; use caution in patients with pre-existing or recent-onset demyelinating disorders. (5.6)
- Hematological Reactions (including leukopenia, pancytopenia and thrombocytopenia): Use with caution in patients who have ongoing, or a history of, significant hematologic abnormalities. Advise patients to seek immediate medical attention if symptoms develop; consider discontinuing CIMZIA in patients with confirmed abnormalities. (5.7)
- Use with Anakinra, Abatacept, Rituximab and Natalizumab: Increased risk of serious infections; concomitant use is not recommended. (5.8, 7.1)
- Autoimmunity: Discontinue CIMZIA if lupus-like syndrome develops. (5.9)
- Live vaccines: Avoid use with CIMZIA (5.10, 7.2)

6 ADVERSE REACTIONS

Most common adverse reactions (≥7%): upper respiratory tract infection, rash, and urinary tract infection (6.1)
To report SUSPECTED ADVERSE REACTIONS, contact UCB, Inc. at 1-866-822-0068 or FDA at 1-800-FDA-1088 or www.fda.gov/medwatch.

7 DRUG INTERACTIONS

Laboratory Tests: May cause erroneously elevated aPTT results. (7.3)

FULL PRESCRIBING INFORMATION

WARNING: SERIOUS INFECTIONS and MALIGNANCY

SERIOUS INFECTIONS

Patients treated with CIMZIA are at increased risk for developing serious infections that may lead to hospitalization or death [see Warnings and Precautions (5.1)and Adverse Reactions (6.1)] . Most patients who developed these infections were taking concomitant immunosuppressants such as methotrexate or corticosteroids.

CIMZIA should be discontinued if a patient develops a serious infection or sepsis.

Reported infections include:

- Active tuberculosis, including reactivation of latent tuberculosis. Patients with tuberculosis have frequently presented with disseminated or extrapulmonary disease. Patients should be tested for latent tuberculosis before CIMZIA use and during therapy. Treatment for latent infection should be initiated prior to CIMZIA use.
- Invasive fungal infections, including histoplasmosis, coccidioidomycosis, candidiasis, aspergillosis, blastomycosis, and pneumocystosis. Patients with histoplasmosis or other invasive fungal infections may present with disseminated, rather than localized disease. Antigen and antibody testing for histoplasmosis may be negative in some patients with active infection. Empiric anti-fungal therapy should be considered in patients at risk for invasive fungal infections who develop severe systemic illness.
- Bacterial, viral and other infections due to opportunistic pathogens, including Legionella and Listeria.

The risks and benefits of treatment with CIMZIA should be carefully considered prior to initiating therapy in patients with chronic or recurrent infection.

Patients should be closely monitored for the development of signs and symptoms of infection during and after treatment with CIMZIA, including the possible development of tuberculosis in patients who tested negative for latent tuberculosis infection prior to initiating therapy. [see Warnings and Precautions (5.1)and Adverse Reactions (6.1)].

MALIGNANCY

Lymphoma and other malignancies, some fatal, have been reported in children and adolescent patients treated with TNF blockers, of which CIMZIA is a member [see Warnings and Precautions (5.2)].

1 INDICATIONS AND USAGE

1.1 Crohn's Disease

CIMZIA is indicated for reducing signs and symptoms of Crohn's disease and maintaining clinical response in adult patients with moderately to severely active disease who have had an inadequate response to conventional therapy.

1.2 Rheumatoid Arthritis

CIMZIA is indicated for the treatment of adults with moderately to severely active rheumatoid arthritis (RA).

1.3 Polyarticular Juvenile Idiopathic Arthritis

CIMZIA is indicated for the treatment of active polyarticular juvenile idiopathic arthritis (pJIA) in patients 2 years of age and older.

1.4 Psoriatic Arthritis

CIMZIA is indicated for the treatment of adult patients with active psoriatic arthritis (PsA).

1.5 Ankylosing Spondylitis

CIMZIA is indicated for the treatment of adults with active ankylosing spondylitis (AS). [see Clinical Studies (14.5)]

1.6 Non-radiographic Axial Spondyloarthritis

CIMZIA is indicated for the treatment of adults with active non-radiographic axial spondyloarthritis (nr-axSpA) with objective signs of inflammation [see Clinical Studies (14.6)].

1.7 Plaque Psoriasis

CIMZIA is indicated for the treatment of adults with moderate-to-severe plaque psoriasis (PsO) who are candidates for systemic therapy or phototherapy [see Clinical Studies (14.7)]

2 DOSAGE AND ADMINISTRATION

CIMZIA is administered by subcutaneous injection .Injection sites should be rotated and injections should not be given into areas where the skin is tender, bruised, red or hard. When a 400 mg dose is needed (given as two subcutaneous injections of 200 mg), injections should occur at separate sites in the thigh or abdomen.

The solution should be carefully inspected visually for particulate matter and discoloration prior to administration. The solution should be a clear to opalescent, colorless to yellow liquid, essentially free from particulates and should not be used if cloudy or if foreign particulate matter is present. CIMZIA does not contain preservatives; therefore, unused portions of drug remaining in the syringe or vial should be discarded.

2.1 Crohn's Disease

The recommended initial adult dose of CIMZIA is 400 mg (given as two subcutaneous injections of 200 mg) initially, and at Weeks 2 and 4. In patients who obtain a clinical response, the recommended maintenance regimen is 400 mg every four weeks.

2.2 Rheumatoid Arthritis

The recommended dose of CIMZIA for adult patients with rheumatoid arthritis is 400 mg (given as two subcutaneous injections of 200 mg) initially and at Weeks 2 and 4, followed by 200 mg every other week. For maintenance dosing, CIMZIA 400 mg every 4 weeks can be considered [see Clinical Studies (14.2)] .

2.3 Polyarticular Juvenile Idiopathic Arthritis

The recommended dose of CIMZIA for patients 2 years of age and older with pJIA is based on weight as shown below.

Weight range (2 years of age and older) | Loading dose | Maintenance dose (beginning at Week 6)
10 kg (22 lbs) to less than 20 kg (44 lbs) | 100 mg at Week 0, 2 and 4 | 50 mg every 2 weeks
20 kg (44 lbs) to less than 40 kg (88 lbs) | 200 mg at Week 0, 2 and 4 | 100 mg every 2 weeks
Greater than or equal to 40 kg (88 lbs) | 400 mg at Week 0, 2 and 4 | 200 mg every 2 weeks

There is no dosage form for Cimzia that allows for patient self-administration for doses below 200 mg. Doses less than 200 mg require administration by a health care professional using the vial kit.

2.4 Psoriatic Arthritis

The recommended dose of CIMZIA for adult patients with psoriatic arthritis is 400 mg (given as 2 subcutaneous injections of 200 mg each) initially and at week 2 and 4, followed by 200 mg every other week. For maintenance dosing, CIMZIA 400 mg every 4 weeks can be considered [see Clinical Studies (14.4)] .

2.5 Ankylosing Spondylitis

The recommended dose of CIMZIA for adult patients with ankylosing spondylitis is 400 mg (given as 2 subcutaneous injections of 200 mg each) initially and at weeks 2 and 4, followed by 200 mg every 2 weeks or 400 mg every 4 weeks.

2.6 Non-radiographic Axial Spondyloarthritis

The recommended dose of CIMZIA for adult patients with non-radiographic axial spondyloarthritis is 400 mg (given as 2 subcutaneous injections of 200 mg each) initially and at weeks 2 and 4, followed by 200 mg every 2 weeks or 400 mg every 4 weeks.

2.7 Plaque Psoriasis

The recommended dose of CIMZIA for adults with moderate-to-severe plaque psoriasis is 400 mg (given as 2 subcutaneous injections of 200 mg each) every other week.

For some patients (with body weight less than or equal to 90 kg), CIMZIA 400 mg (given as 2 subcutaneous injections of 200 mg each) initially and at Weeks 2 and 4, followed by 200 mg every other week can be considered [see Clinical Studies (14.7)] .

2.8 Preparation and Administration of CIMZIA Using the Lyophilized Powder for Injection

CIMZIA Lyophilized powder should be prepared and administered by a health care professional. CIMZIA is provided in a package that contains everything required to reconstitute and inject the drug [see How Supplied/Storage and Handling (16)] . Step-by-step preparation and administration instructions are provided below.

Preparation and Storage

1. If refrigerated, remove CIMZIA from the refrigerator and allow the vial(s) to sit at room temperature for 30 minutes before reconstituting. Do not warm the vial in any other way. Use appropriate aseptic technique when preparing and administering CIMZIA.
2. Reconstitute the vial(s) of CIMZIA with 1 mL of Sterile Water for Injection, USP using the 20-gauge needle provided. The sterile water for injection should be directed at the vial wall rather than directly on CIMZIA.
3. Gently swirl each vial of CIMZIA for about one minute without shaking, assuring that all of the powder comes in contact with the Sterile Water for Injection. The swirling should be as gentle as possible in order to avoid creating a foaming effect.
4. Continue swirling every 5 minutes as long as non-dissolved particles are observed. Full reconstitution may take as long as 30 minutes. The final reconstituted solution contains 200 mg/mL and should be clear to opalescent, colorless to yellow liquid essentially free from particulates.
5. Once reconstituted, CIMZIA can be stored in the vials for up to 24 hours between 2° to 8° C (36° to 46° F) prior to injection. Do not freeze.

Administration

1. Prior to injecting, reconstituted CIMZIA should be at room temperature but do not leave reconstituted CIMZIA at room temperature for more than two hours prior to administration.
2. Withdraw the reconstituted solution into a separate syringe for each vial using a new 20-gauge needle for each vial so that each syringe contains the required volume of CIMZIA [see Dosage and Administration (2.1-2.7)].
3. Replace the 20-gauge needle(s) on the syringes with a 23-gauge(s) for administration.
4. Inject the full contents of the syringe(s) subcutaneously, by pinching the skin of the thigh or abdomen. Where a 400 mg dose is required, two injections are required, therefore, separate sites should be used for each 200 mg injection.

2.9 Preparation and Administration of CIMZIA Using the Prefilled Syringe

After proper training in subcutaneous injection technique, a patient may self-inject with the CIMZIA Prefilled Syringe if a physician determines that it is appropriate.

- If refrigerated, remove the prefilled syringe from the carton and let it warm to room temperature.
- Inspect the liquid in the prefilled syringe. It should be clear to opalescent and colorless to yellow and free from particulates. Discard the syringe if cloudy, discolored or contains particulates.
- Suitable sites for injection include the thigh or abdomen at least 2 inches away from the navel. Inject at least 1 inch from the previous site.
- Do not inject into areas where the skin is tender, bruised, red or hard, or where there are scars or stretch marks.

The needle shield inside the removable cap of the CIMZIA prefilled syringe contains a derivative of natural rubber latex which may cause allergic reactions and should be handled with caution by latex-sensitive individuals [see Warnings and Precautions (5.4)] .

2.10 Monitoring to Assess Safety

Before initiation of therapy with CIMZIA, all patients must be evaluated for both active and inactive (latent) tuberculosis infection. The possibility of undetected latent tuberculosis should be considered in patients who have immigrated from or traveled to countries with a high prevalence of tuberculosis or had close contact with a person with active tuberculosis. Appropriate screening tests (e.g. tuberculin skin test and chest x-ray) should be performed in all patients.

2.11 Concomitant Medications

CIMZIA may be used as monotherapy or concomitantly with non-biological disease modifying anti-rheumatic drugs (DMARDs).

The use of CIMZIA in combination with biological DMARDs or other tumor necrosis factor (TNF) blocker therapy is not recommended.

3 DOSAGE FORMS AND STRENGTHS

For Injection: 200 mg of white to off-white lyophilized powder in a single-dose vial for reconstitution

Injection: 200 mg/mL clear to opalescent, colorless to yellow solution in a single-dose prefilled syringe

4 CONTRAINDICATIONS

CIMZIA is contraindicated in patients with a history of hypersensitivity reaction to certolizumab pegol or to any of the excipients. Reactions have included angioedema, anaphylaxis, serum sickness, and urticaria [see Warnings and Precautions (5.4)] .

5 WARNINGS AND PRECAUTIONS

5.1 Risk of Serious Infections

Patients treated with CIMZIA are at an increased risk for developing serious infections involving various organ systems and sites that may lead to hospitalization or death.

Opportunistic infections due to bacterial, mycobacterial, invasive fungal, viral, parasitic, or other opportunistic pathogens including aspergillosis, blastomycosis, candidiasis, coccidioidomycosis, histoplasmosis, legionellosis, listeriosis, pneumocystosis and tuberculosis have been reported with TNF blockers. Patients have frequently presented with disseminated rather than localized disease.

Treatment with CIMZIA should not be initiated in patients with an active infection, including clinically important localized infections. Patients greater than 65 years of age, patients with co-morbid conditions, and/or patients taking concomitant immunosuppressants (e.g. corticosteroids or methotrexate) may be at a greater risk of infection. The risks and benefits of treatment should be considered prior to initiating therapy in patients:

- with chronic or recurrent infection
- who have been exposed to tuberculosis
- with a history of an opportunistic infection
- who have resided or traveled in areas of endemic tuberculosis or endemic mycoses, such as histoplasmosis, coccidioidomycosis, or blastomycosis
- with underlying conditions that may predispose them to infection

Tuberculosis

Cases of reactivation of tuberculosis or new tuberculosis infections have been observed in patients receiving CIMZIA, including patients who have previously or concomitantly received treatment for latent or active tuberculosis. Reports included cases of pulmonary and extrapulmonary (i.e., disseminated) tuberculosis. Evaluate patients for tuberculosis risk factors and test for latent infection prior to initiating CIMZIA and periodically during therapy.

Treatment of latent tuberculosis infection prior to therapy with TNF-blocking agents has been shown to reduce the risk of tuberculosis reactivation during therapy. Prior to initiating CIMZIA, assess if treatment for latent tuberculosis is needed; and consider an induration of 5 mm or greater a positive tuberculin skin test result, even for patients previously vaccinated with Bacille Calmette-Guerin (BCG).

Consider anti-tuberculosis therapy prior to initiation of CIMZIA in patients with a past history of latent or active tuberculosis in whom an adequate course of treatment cannot be confirmed, and for patients with a negative test for latent tuberculosis but having risk factors for tuberculosis infection. Despite previous or concomitant treatment for latent tuberculosis, cases of active tuberculosis have occurred in patients treated with CIMZIA. Some patients who have been successfully treated for active tuberculosis have redeveloped tuberculosis while being treated with CIMZIA. Consultation with a physician with expertise in the treatment of tuberculosis is recommended to aid in the decision of whether initiating anti-tuberculosis therapy is appropriate for an individual patient.

Strongly consider tuberculosis in patients who develop a new infection during CIMZIA treatment, especially in patients who have previously or recently traveled to countries with a high prevalence of tuberculosis, or who have had close contact with a person with active tuberculosis.

Monitoring

Patients should be closely monitored for the development of signs and symptoms of infection during and after treatment with CIMZIA, including the development of tuberculosis in patients who tested negative for latent tuberculosis infection prior to initiating therapy. Tests for latent tuberculosis infection may also be falsely negative while on therapy with CIMZIA.

CIMZIA should be discontinued if a patient develops a serious infection or sepsis. A patient who develops a new infection during treatment with CIMZIA should be closely monitored, undergo a prompt and complete diagnostic workup appropriate for an immunocompromised patient, and appropriate antimicrobial therapy should be initiated.

Invasive Fungal Infections

For patients who reside or travel in regions where mycoses are endemic, invasive fungal infection should be suspected if they develop a serious systemic illness. Appropriate empiric antifungal therapy should be considered while a diagnostic workup is being performed. Antigen and antibody testing for histoplasmosis may be negative in some patients with active infection. When feasible, the decision to administer empiric antifungal therapy in these patients should be made in consultation with a physician with expertise in the diagnosis and treatment of invasive fungal infections and should take into account both the risk for severe fungal infection and risks of antifungal therapy.

5.2 Malignancies

In the controlled portions of clinical studies of some TNF blockers, more cases of malignancies have been observed among patients receiving TNF blockers compared to control patients. During controlled and open-labeled portions of CIMZIA studies of Crohn's disease and other diseases, malignancies (excluding non-melanoma skin cancer) were observed at a rate (95% confidence interval) of 0.5 (0.4, 0.7) per 100 patient-years among 4,650 CIMZIA-treated patients versus a rate of 0.6 (0.1, 1.7) per 100 patient-years among 1,319 placebo-treated patients. During CIMZIA studies of psoriasis, malignancies (excluding non-melanoma skin cancer) were observed corresponding to an incidence rate of 0.5 (0.2, 1.0) per 100 subject-years among a total of 995 subjects who received CIMZIA. The size of the control group and limited duration of the controlled portions of the studies precludes the ability to draw firm conclusions.

Malignancies, some fatal, have been reported among children, adolescents, and young adults who received treatment with TNF-blocking agents (initiation of therapy ≤ 18 years of age), of which CIMZIA is a member. Approximately half the cases were lymphomas, including Hodgkin's and non-Hodgkin's lymphoma. The other cases represented a variety of different malignancies and included rare malignancies usually associated with immunosuppression and malignancies that are not usually observed in children and adolescents. The malignancies occurred after a median of 30 months of therapy (range 1 to 84 months). Most of the patients were receiving concomitant immunosuppressants. These cases were reported post-marketing and are derived from a variety of sources including registries and spontaneous post-marketing reports.

In the controlled portions of clinical trials of all the TNF blockers, more cases of lymphoma have been observed among patients receiving TNF blockers compared to control patients. In controlled studies of CIMZIA for Crohn's disease and other investigational uses, there was one case of lymphoma among 2,657 Cimzia-treated patients and one case of Hodgkin's lymphoma among 1,319 placebo-treated patients.

In the CIMZIA RA clinical trials (placebo-controlled and open-label) a total of three cases of lymphoma were observed among 2,367 patients. This is approximately 2-fold higher than expected in the general population. Patients with RA, particularly those with highly active disease, are at a higher risk for the development of lymphoma. In the CIMZIA PsO clinical trials (placebo-controlled and open-label) there was one case of Hodgkin's lymphoma.

Rates in clinical studies for CIMZIA cannot be compared to the rates of clinical trials of other TNF blockers and may not predict the rates observed when CIMZIA is used in a broader patient population. Patients with Crohn's disease that require chronic exposure to immunosuppressant therapies may be at higher risk than the general population for the development of lymphoma, even in the absence of TNF blocker therapy [see Adverse Reactions (6.1)] . The potential role of TNF blocker therapy in the development of malignancies in adults is not known.

Postmarketing cases of hepatosplenic T-cell lymphoma (HSTCL), a rare type of T-cell lymphoma that has a very aggressive disease course and is usually fatal, have been reported in patients treated with TNF blockers, including CIMZIA. The majority of reported TNF blocker cases occurred in adolescent and young adult males with Crohn's disease or ulcerative colitis. Almost all of these patients had received treatment with the immunosuppressants azathioprine and/or 6-mercaptopurine (6-MP) concomitantly with a TNF blocker at or prior to diagnosis. It is uncertain whether the occurrence of HSTCL is related to use of a TNF blocker or a TNF blocker in combination with these other immunosuppressants. The potential risk of using a TNF blocker in combination with azathioprine or 6-MP should be carefully considered.

Cases of acute and chronic leukemia have been reported in association with post-marketing TNF-blocker use in RA and other indications. Even in the absence of TNF-blocker therapy, patients with RA may be at a higher risk (approximately 2-fold) than the general population for the development of leukemia.

Melanoma and Merkel cell carcinoma have been reported in patients treated with TNF blockers, including CIMZIA. Periodic skin examinations are recommended for all patients, particularly those with risk factors for skin cancer.

5.3 Heart Failure

Cases of worsening congestive heart failure (CHF) and new onset CHF have been reported with TNF blockers, including CIMZIA. CIMZIA has not been formally studied in patients with CHF; however, in clinical studies in patients with CHF with another TNF blocker, worsening congestive heart failure (CHF) and increased mortality due to CHF were observed. Exercise caution in patients with heart failure and monitor them carefully [see Adverse Reactions (6.1)].

5.4 Hypersensitivity Reactions

The following symptoms that could be compatible with hypersensitivity reactions have been reported rarely following CIMZIA administration to patients: angioedema, anaphylaxis, dyspnea, hypotension, rash, serum sickness, and urticaria. Some of these reactions occurred after the first administration of CIMZIA. If such reactions occur, discontinue further administration of CIMZIA and institute appropriate therapy. There are no data on the risks of using CIMZIA in patients who have experienced a severe hypersensitivity reaction towards another TNF blocker; in these patients caution is needed [see Adverse Reactions (6.1)] .

The needle shield inside the removable cap of the CIMZIA prefilled syringe contains a derivative of natural rubber latex which may cause an allergic reaction in individuals sensitive to latex.

5.5 Hepatitis B Virus Reactivation

Use of TNF blockers, including CIMZIA, has been associated with reactivation of hepatitis B virus (HBV) in patients who are chronic carriers of this virus. In some instances, HBV reactivation occurring in conjunction with TNF blocker therapy has been fatal. The majority of reports have occurred in patients concomitantly receiving other medications that suppress the immune system, which may also contribute to HBV reactivation.

Test patients for HBV infection before initiating treatment with CIMZIA. For patients who test positive for HBV infection, consultation with a physician with expertise in the treatment of hepatitis B is recommended. Adequate data are not available on the safety or efficacy of treating patients who are carriers of HBV with anti-viral therapy in conjunction with TNF blocker therapy to prevent HBV reactivation. Patients who are carriers of HBV and require treatment with CIMZIA should be closely monitored for clinical and laboratory signs of active HBV infection throughout therapy and for several months following termination of therapy.

In patients who develop HBV reactivation, discontinue CIMZIA and initiate effective anti-viral therapy with appropriate supportive treatment. The safety of resuming TNF blocker therapy after HBV reactivation is controlled is not known. Therefore, exercise caution when considering resumption of CIMZIA therapy in this situation and monitor patients closely.

5.6 Neurologic Reactions

Use of TNF blockers, of which CIMZIA is a member, has been associated with rare cases of new onset or exacerbation of clinical symptoms and/or radiographic evidence of central nervous system demyelinating disease, including multiple sclerosis, and with peripheral demyelinating disease, including Guillain-Barré syndrome. Exercise caution in considering the use of CIMZIA in patients with pre-existing or recent-onset central or peripheral nervous system demyelinating disorders. Rare cases of neurological disorders, including seizure disorder, optic neuritis, and peripheral neuropathy have been reported in patients treated with CIMZIA [see Adverse Reactions (6.1)] .

5.7 Hematological Reactions

Rare reports of pancytopenia, including aplastic anemia, have been reported with TNF blockers. Adverse reactions of the hematologic system, including medically significant cytopenia (e.g., leukopenia, pancytopenia, thrombocytopenia) have been infrequently reported with CIMZIA [see Adverse Reactions (6.1)] . The causal relationship of these events to CIMZIA remains unclear.

Although no high risk group has been identified, exercise caution in patients being treated with CIMZIA who have ongoing, or a history of, significant hematologic abnormalities. Advise all patients to seek immediate medical attention if they develop signs and symptoms suggestive of blood dyscrasias or infection (e.g., persistent fever, bruising, bleeding, pallor) while on CIMZIA. Consider discontinuation of CIMZIA therapy in patients with confirmed significant hematologic abnormalities.

5.8 Use with Biological Disease-Modifying Antirheumatic Drugs (Biological DMARDs)

Serious infections were seen in clinical studies with concurrent use of anakinra (an interleukin-1 antagonist) and another TNF blocker, etanercept, with no added benefit compared to etanercept alone. A higher risk of serious infections was also observed in combination use of TNF blockers with abatacept and rituximab. Because of the nature of the adverse events seen with this combination therapy, similar toxicities may also result from the use of CIMZIA in this combination. Therefore, the use of CIMZIA in combination with other biological DMARDs is not recommended [see Drug Interactions (7.1)].

5.9 Autoimmunity

Treatment with CIMZIA may result in the formation of autoantibodies and rarely, in the development of a lupus-like syndrome. If a patient develops symptoms suggestive of a lupus-like syndrome following treatment with CIMZIA, discontinue treatment [see Adverse Reactions (6.1)] .

5.10 Immunizations

Avoid use of live vaccines during or immediately prior to initiation of therapy with CIMZIA. Update immunizations in agreement with current immunization guidelines prior to initiating CIMZIA therapy.

In a placebo-controlled clinical trial of patients with rheumatoid arthritis, no difference was detected in antibody response to vaccine between CIMZIA and placebo treatment groups when the pneumococcal polysaccharide vaccine and influenza vaccine were administered concurrently with CIMZIA. Similar proportions of patients developed protective levels of anti-vaccine antibodies between CIMZIA and placebo treatment groups; however patients receiving CIMZIA and concomitant methotrexate had a lower humoral response compared with patients receiving CIMZIA alone. The clinical significance of this is unknown.

5.11 Immunosuppression

Since TNF mediates inflammation and modulates cellular immune responses, the possibility exists for TNF blockers, including CIMZIA, to affect host defenses against infections and malignancies. The impact of treatment with CIMZIA on the development and course of malignancies, as well as active and/or chronic infections, is not fully understood [see Warnings and Precautions (5.1, 5.2, 5.5)and Adverse Reactions (6.1)] . The safety and efficacy of CIMZIA in patients with immunosuppression has not been formally evaluated.

6 ADVERSE REACTIONS

The most serious adverse reactions were:

- Serious Infections [see Warnings and Precautions (5.1)]
- Malignancies [see Warnings and Precautions (5.2)]
- Heart Failure [see Warnings and Precautions (5.3)]
- Hypersensitivity Reactions [see Warnings and Precautions (5.4)]
- Hepatitis B Virus Reactivation [see Warnings and Precautions (5.5)]
- Neurologic Reactions [see Warnings and Precautions (5.6)]
- Hematologic Reactions [see Warnings and Precautions (5.7)]
- Autoimmunity [see Warnings and Precautions (5.9)]
- Immunosuppression [see Warnings and Precautions (5.11)]

6.1 Clinical Trials Experience

Because clinical studies are conducted under widely varying and controlled conditions, adverse reaction rates observed in clinical studies of a drug cannot be directly compared to rates in the clinical studies of another drug, and may not predict the rates observed in a broader patient population in clinical practice.

In premarketing controlled trials of all adult patient populations combined the most common adverse reactions (≥ 8%) were upper respiratory infections (18%), rash (9%) and urinary tract infections (8%).

Adverse Reactions Most Commonly Leading to Discontinuation of Treatment in Premarketing Controlled Trials

The proportion of patients with Crohn's disease who discontinued treatment due to adverse reactions in the controlled clinical studies was 8% for CIMZIA and 7% for placebo. The most common adverse reactions leading to the discontinuation of CIMZIA (for at least 2 patients and with a higher incidence than placebo) were abdominal pain (0.4% CIMZIA, 0.2% placebo), diarrhea (0.4% CIMZIA, 0% placebo), and intestinal obstruction (0.4% CIMZIA, 0% placebo).

The proportion of patients with rheumatoid arthritis who discontinued treatment due to adverse reactions in the controlled clinical studies was 5% for CIMZIA and 2.5% for placebo. The most common adverse reactions leading to discontinuation of CIMZIA were tuberculosis infections (0.5%); and pyrexia, urticaria, pneumonia, and rash (0.3%).

Controlled Studies with Crohn's Disease

The data described below reflect exposure to CIMZIA at 400 mg subcutaneous dosing in studies of patients with Crohn's disease. In the safety population in controlled studies, a total of 620 patients with Crohn's disease received CIMZIA at a dose of 400 mg, and 614 subjects received placebo (including subjects randomized to placebo in Study CD2 following open-label dosing of CIMZIA at Weeks 0, 2, 4). In controlled and uncontrolled studies, 1,564 patients received CIMZIA at some dose level, of whom 1,350 patients received 400 mg CIMZIA. Approximately 55% of subjects were female, 45% were male, and 94% were Caucasian. The majority of patients in the active group were between the ages of 18 and 64.

During controlled clinical studies, the proportion of patients with serious adverse reactions was 10% for CIMZIA and 9% for placebo. The most common adverse reactions (occurring in ≥ 5% of CIMZIA-treated patients, and with a higher incidence compared to placebo) in controlled clinical studies with CIMZIA were upper respiratory infections (e.g. nasopharyngitis, laryngitis, viral infection) in 20% of CIMZIA-treated patients and 13% of placebo-treated patients, urinary tract infections (e.g. bladder infection, bacteriuria, cystitis) in 7% of CIMZIA-treated patients and in 6% of placebo-treated patients, and arthralgia (6% CIMZIA, 4% placebo).

Other Adverse Reactions

The most commonly occurring adverse reactions in controlled trials of Crohn's disease were described above. Other serious or significant adverse reactions reported in controlled and uncontrolled studies in Crohn's disease and other diseases, occurring in patients receiving CIMZIA at doses of 400 mg or other doses include:

Blood and lymphatic system disorders:Anemia, leukopenia, lymphadenopathy, pancytopenia, and thrombophilia.

Cardiac disorders:Angina pectoris, arrhythmias, atrial fibrillation, cardiac failure, hypertensive heart disease, myocardial infarction, myocardial ischemia, pericardial effusion, pericarditis, stroke and transient ischemic attack.

Eye disorders:Optic neuritis, retinal hemorrhage, and uveitis.

General disorders and administration site conditions:Bleeding and injection site reactions.

Hepatobiliary disorders: Elevated liver enzymes and hepatitis.

Immune system disorders: Alopecia totalis.

Psychiatric disorders:Anxiety, bipolar disorder, and suicide attempt.

Renal and urinary disorders:Nephrotic syndrome and renal failure.

Reproductive system and breast disorders:Menstrual disorder.

Skin and subcutaneous tissue disorders:Dermatitis, erythema nodosum, and urticaria.

Vascular disorders:Thrombophlebitis, vasculitis.

Controlled Studies with Rheumatoid Arthritis

CIMZIA was studied primarily in placebo-controlled trials and in long-term follow-up studies. The data described below reflect the exposure to CIMZIA in 2,367 RA patients, including 2,030 exposed for at least 6 months, 1,663 exposed for at least one year and 282 for at least 2 years; and 1,774 in adequate and well-controlled studies. In placebo-controlled studies, the population had a median age of 53 years at entry; approximately 80% were females, 93% were Caucasian and all patients were suffering from active rheumatoid arthritis, with a median disease duration of 6.2 years. Most patients received the recommended dose of CIMZIA or higher.

Table 1 summarizes the reactions reported at a rate of at least 3% in patients treated with CIMZIA 200 mg every other week compared to placebo (saline formulation), given concomitantly with methotrexate.

Table 1: Adverse Reactions Reported by ≥3% of Patients Treated with CIMZIA Dosed Every Other Week during Placebo-Controlled Period of Rheumatoid Arthritis Studies, with Concomitant Methotrexate.
Adverse Reaction (Preferred Term) | Placebo+ MTX [EOW = Every other Week, MTX = Methotrexate.] (%) N =324 | CIMZIA 200 mg EOW + MTX(%) N =640
Upper respiratory tract infection | 2 | 6
Headache | 4 | 5
Hypertension | 2 | 5
Nasopharyngitis | 1 | 5
Back pain | 1 | 4
Pyrexia | 2 | 3
Pharyngitis | 1 | 3
Rash | 1 | 3
Acute bronchitis | 1 | 3
Fatigue | 2 | 3

Hypertensive adverse reactions were observed more frequently in patients receiving CIMZIA than in controls. These adverse reactions occurred more frequently among patients with a baseline history of hypertension and among patients receiving concomitant corticosteroids and non-steroidal anti-inflammatory drugs (NSAIDs).

Patients receiving CIMZIA 400 mg as monotherapy every 4 weeks in rheumatoid arthritis controlled clinical trials had similar adverse reactions to those patients receiving CIMZIA 200 mg every other week.

Other Adverse Reactions

Other infrequent adverse reactions (occurring in less than 3% of RA patients) were similar to those seen in Crohn's disease patients.

Polyarticular Juvenile Idiopathic Arthritis Clinical Study

CIMZIA has been studied in 193 patients with juvenile idiopathic arthritis (JIA) with active polyarthritis aged 2 years and older. In general, the safety profile for pediatric patients with JIA with active polyarthritis was similar to the safety profile seen in adult RA patients treated with CIMZIA.

Psoriatic Arthritis Clinical Study

CIMZIA has been studied in 409 patients with psoriatic arthritis (PsA) in a placebo-controlled trial. The safety profile for patients with PsA treated with CIMZIA was similar to the safety profile seen in patients with RA and previous experience with CIMZIA .

Ankylosing Spondylitis Clinical Study

CIMZIA has been studied in 325 patients with axial spondyloarthritis of whom the majority had ankylosing spondylitis (AS) in a placebo-controlled study (AS-1). The safety profile for patients in study AS-1 treated with CIMZIA was similar to the safety profile seen in patients with RA.

Non-radiographic Axial Spondyloarthritis Clinical Study

CIMZIA has been studied in 317 patients with non-radiographic axial spondyloarthritis (nr-axSpA-1). The safety profile for patients with nr-axSpA treated with CIMZIA was similar to the safety profile seen in patients with RA and previous experience with CIMZIA.

Plaque Psoriasis Clinical Studies

In clinical studies, a total of 1112 subjects with plaque psoriasis were treated with CIMZIA. Of these, 779 subjects were exposed for at least 12 months, 551 for 18 months, and 66 for 24 months.

Data from three placebo-controlled studies (Studies PS-1, PS-2, and PS-3) in 1020 subjects (mean age 46 years, 66% males, 94% white) were pooled to evaluate the safety of CIMZIA [see Clinical Studies (14.7)] .

Placebo-Controlled Period (Week 0-16)

In the placebo-controlled period of Studies PS-1, PS-2 and PS-3 in the 400 mg group, adverse events occurred in 63.5% of subjects in the CIMZIA group compared to 61.8% of subjects in the placebo group. The rates of serious adverse events were 4.7% in the CIMZIA group and 4.5% in the placebo group. Table 2 summarizes the adverse reactions that occurred at a rate of at least 1% and at a higher rate in the CIMZIA group than in the placebo group.

Table 2: Adverse Reactions Occurring in ≥1% of Subjects in the CIMZIA Group and More Frequently than in the Placebo Group in the Plaque Psoriasis Studies PS-1, PS-2, and PS-3.
Adverse Reactions | Cimzia 400 mg every other week n (%) N=342 | Cimzia 200 mg [Subjects received 400 mg of CIMZIA at Weeks 0, 2, and 4, followed by 200 mg every other week.] every other week n (%) N=350 | Placebo n (%) N=157
Upper respiratory tract infections [Upper respiratory tract infection cluster includes upper respiratory tract infection, pharyngitis bacterial, pharyngitis streptococcal, upper respiratory tract infection bacterial, viral upper respiratory tract infection, viral pharyngitis, viral sinusitis, and nasopharyngitis.] | 75 (21.9) | 68 (19.4) | 33 (21.0)
Headache [Headache includes headache and tension headache.] | 13 (3.8) | 10 (2.9) | 4 (2.5)
Injection site reactions [Injection site reactions cluster includes injection site reaction, injection site erythema, injection site bruising, injection site discoloration, injection site pain, and injection site swelling.] | 11 (3.2) | 6 (1.7) | 1 (0.6)
Cough | 11 (3.2) | 4 (1.1) | 3 (1.9)
Herpes infections [Herpes infections cluster includes oral herpes, herpes dermatitis, herpes zoster, and herpes simplex.] | 5 (1.5) | 5 (1.4) | 2 (1.3)

Elevated Liver Enzymes

Elevated liver enzymes were reported more frequently in the CIMZIA-treated subjects (4.3% in the 200 mg group and 2.3% in the 400 mg group) than in the placebo-treated subjects (2.5%). Of CIMZIA-treated subjects who had elevation of liver enzymes, two subjects were discontinued from the trial. In controlled Phase 3 studies of CIMZIA in adults with PsO with a controlled period duration ranging from 0 to 16 weeks, AST and/or ALT elevations ≥5 × ULN occurred in 0.9% of CIMZIA 200 mg or CIMZIA 400 mg arms and none in placebo arm.

Psoriasis-Related Adverse Events

In controlled clinical studies in psoriasis, change of plaque psoriasis into a different psoriasis sub-types (including erythrodermic, pustular and guttate), was observed in <1% of Cimzia treated subjects.

Adverse Reactions of Special Interest Across Indications

Infections

The incidence of infections in controlled studies in Crohn's disease was 38% for CIMZIA-treated patients and 30% for placebo-treated patients. The infections consisted primarily of upper respiratory infections (20% for CIMZIA, 13% for placebo). The incidence of serious infections during the controlled clinical studies was 3% per patient-year for CIMZIA-treated patients and 1% for placebo-treated patients. Serious infections observed included bacterial and viral infections, pneumonia, and pyelonephritis.

The incidence of new cases of infections in controlled clinical studies in rheumatoid arthritis was 0.91 per patient-year for all CIMZIA-treated patients and 0.72 per patient-year for placebo-treated patients. The infections consisted primarily of upper respiratory tract infections, herpes infections, urinary tract infections, and lower respiratory tract infections. In the controlled rheumatoid arthritis studies, there were more new cases of serious infection adverse reactions in the CIMZIA treatment groups, compared to the placebo groups (0.06 per patient-year for all CIMZIA doses vs. 0.02 per patient-year for placebo). Rates of serious infections in the 200 mg every other week dose group were 0.06 per patient-year and in the 400 mg every 4 weeks dose group were 0.04 per patient-year. Serious infections included tuberculosis, pneumonia, cellulitis, and pyelonephritis. In the placebo group, no serious infection occurred in more than one subject. There is no evidence of increased risk of infections with continued exposure over time [see Warnings and Precautions (5.1)] .

In controlled clinical studies in psoriasis, the incidence rates of infections were similar in the CIMZIA and placebo groups. The infections consisted primarily of upper respiratory tract infections and viral infections (including herpes infections). Serious adverse events of infection occurred in CIMZIA-treated patients during the placebo-controlled periods of the pivotal studies (pneumonia, abdominal abscess, and hematoma infection) and Phase 2 study (urinary tract infection, gastroenteritis, and disseminated tuberculosis).

In an open-label clinical study of 193 pediatric patients with JIA with active polyarthritis, there were 26 serious infections; the most frequently reported serious infection was pneumonia.

Tuberculosis and Opportunistic Infections

In completed and ongoing global clinical studies in all indications including 5,118 CIMZIA-treated patients, the overall rate of tuberculosis is approximately 0.61 per 100 patient-years across all indications.

The majority of cases occurred in countries with high endemic rates of TB. Reports include cases of disseminated (miliary, lymphatic, and peritoneal) as well as pulmonary TB. The median time to onset of TB for all patients exposed to CIMZIA across all indications was 345 days. In the studies with CIMZIA in RA, there were 36 cases of TB among 2,367 exposed patients, including some fatal cases. Rare cases of opportunistic infections have also been reported in these clinical trials. In Phase 2 and Phase 3 studies with CIMZIA in plaque psoriasis, there were 2 cases of TB among 1112 exposed patients [see Warnings and Precautions (5.1)].

In an open-label clinical study of 193 pediatric patients with JIA with active polyarthritis, opportunistic infections consisted of tuberculosis, liver tuberculosis, varicella, pneumonia fungal, and esophageal candidiasis. Two cases of disseminated tuberculosis (liver TB and disseminated TB) were fatal.

Malignancies

In clinical studies of CIMZIA, the overall incidence rate of malignancies was similar for CIMZIA-treated and control patients. For some TNF blockers, more cases of malignancies have been observed among patients receiving those TNF blockers compared to control patients [see Warnings and Precautions (5.2)].

Heart Failure

In placebo-controlled and open-label studies, cases of new or worsening heart failure have been reported for CIMZIA-treated patients. The majority of these cases were mild to moderate and occurred during the first year of exposure [see Warnings and Precautions (5.3)].

Hypersensitivity Reactions

The following symptoms that could be compatible with hypersensitivity reactions have been reported rarely following CIMZIA administration to patients: angioedema, allergic dermatitis, dizziness (postural), dyspnea, hot flush, hypotension, injection site reactions, malaise, pyrexia, rash, serum sickness, and (vasovagal) syncope [see Warnings and Precautions (5.4)] .

Autoantibodies

In clinical studies in Crohn's disease, 4% of patients treated with CIMZIA and 2% of patients treated with placebo that had negative baseline ANA titers developed positive titers during the studies. One of the 1,564 Crohn's disease patients treated with CIMZIA developed symptoms of a lupus-like syndrome.

In clinical trials of TNF blockers, including CIMZIA, in patients with RA, some patients have developed ANA. Four patients out of 2,367 patients treated with CIMZIA in RA clinical studies developed clinical signs suggestive of a lupus-like syndrome. The impact of long-term treatment with CIMZIA on the development of autoimmune diseases is unknown [see Warnings and Precautions (5.9)].

In a clinical study in pediatric patients with JIA with active polyarthritis, 17.1% of patients treated with CIMZIA that had negative baseline ANA titers developed positive titers during the study. 1.1% of the patients developed anti-dsDNA antibodies during the study; no patients developed symptoms of a lupus-like syndrome.

6.2 Immunogenicity

The observed incidence of anti-drug antibodies is highly dependent on the sensitivity and specificity of the assay. Differences in assay methods preclude meaningful comparisons of the incidence of anti-drug antibodies in the studies described below with the incidence of anti-drug antibodies in other studies, including those of certolizumab pegol or of other certolizumab products.

Patients with Crohn's disease were tested at multiple time points for antibodies to certolizumab pegol during Studies CD1 and CD2. In patients continuously exposed to CIMZIA, the overall percentage of patients who were antibody positive to CIMZIA on at least one occasion was 8%; approximately 6% were neutralizing in vitro. No apparent correlation of antibody development to adverse events or efficacy was observed. Patients treated with concomitant immunosuppressants had a lower rate of antibody development than patients not taking immunosuppressants at baseline (3% and 11%, respectively). The following adverse events were reported in Crohn's disease patients who were antibody-positive (N = 100) at an incidence at least 3% higher compared to antibody-negative patients (N = 1,242): abdominal pain, arthralgia, edema peripheral, erythema nodosum, injection site erythema, injection site pain, pain in extremity, and upper respiratory tract infection.

In two long-term (up to 7 years of exposure), open-label Crohn's disease studies, overall 23% (207/903) of patients developed antibodies against certolizumab pegol on at least one occasion. Of the 207 patients who were antibody positive, 152 (73%) had a persistent reduction of drug plasma concentration, which represents 17% (152/903) of the study population. The data from these two studies do not suggest an association between the development of antibodies and adverse events.

The overall percentage of patients with antibodies to certolizumab pegol detectable on at least one occasion was 7% (105 of 1,509) in the rheumatoid arthritis placebo-controlled trials. Approximately one third (3%, 39 of 1,509) of these patients had antibodies with neutralizing activity in vitro. Patients treated with concomitant immunosuppressants (MTX) had a lower rate of antibody development than patients not taking immunosuppressants at baseline. Patients treated with concomitant immunosuppressant therapy (MTX) in RA-I, RA-II, RA-III had a lower rate of neutralizing antibody formation overall than patients treated with CIMZIA monotherapy in RA-IV (2% vs. 8%). Both the loading dose of 400 mg every other week at Weeks 0, 2 and 4 and concomitant use of MTX were associated with reduced immunogenicity.

Antibody formation was associated with lowered drug plasma concentration and reduced efficacy. In patients receiving the recommended CIMZIA dosage of 200 mg every other week with concomitant MTX, the ACR20 response was lower among antibody positive patients than among antibody-negative patients (Study RA-I, 48% versus 60%; Study RA-II 35% versus 59%, respectively). In Study RA-III, too few patients developed antibodies to allow for meaningful analysis of ACR20 response by antibody status. In Study RA-IV (monotherapy), the ACR20 response was 33% versus 56%, antibody-positive versus antibody-negative status, respectively [see Clinical Pharmacology (12.3)]. No association was seen between antibody development and the development of adverse events.

Approximately 8 % (22/265) and 19% (54/281) of subjects with psoriasis who received CIMZIA 400 mg every 2 weeks and CIMZIA 200 mg every 2 weeks for 48 weeks, respectively, developed antibodies to certolizumab pegol. Of the subjects who developed antibodies to certolizumab pegol, 45% (27/60) had antibodies that were classified as neutralizing. Antibody formation was associated with lowered drug plasma concentration and reduced efficacy.

A more sensitive and drug tolerant electrochemiluminesence (ECL)-based bridging assay was used for the first time in the nr-axSpA-1 study, resulting in a greater proportion of samples having measurable antibodies to certolizumab pegol and thus a greater incidence of patients being classed as antibody positive. In the placebo-controlled trial in patients with non-radiographic axial spondyloarthritis, after up to 52 weeks of treatment, the overall incidence of patients who were antibody positive to certolizumab pegol was 97% (248/255 patients). Of these antibody positive patients, higher titers were associated with reduced certolizumab pegol plasma levels.

The data above reflect the percentage of patients whose test results were considered positive for antibodies to certolizumab pegol in an ELISA or ECL-based bridging assay, and are highly dependent on the sensitivity and specificity of the assay.

In a clinical study of pediatric patients with JIA with active polyarthritis, immunogenicity was evaluated using an ECL-based assay. For the patients receiving the recommended CIMZIA dose, the incidence of treatment emergent-anti-certolizumab pegol antibody positivity was 92.4% for the entire treatment period. Of these antibody positive patients, higher titers were associated with reduced certolizumab pegol plasma levels.

6.3 Postmarketing Experience

The following adverse reactions have been identified during post-approval use of CIMZIA. Because these reactions are reported voluntarily from a population of uncertain size, it is not always possible to estimate reliably their frequency or establish a causal relationship to drug exposure.

Vascular disorder: systemic vasculitis has been identified during post-approval use of TNF blockers.

Skin: case of severe skin reactions, including Stevens-Johnson syndrome, toxic epidermal necrolysis, erythema multiforme, new or worsening psoriasis (all sub-types including pustular and palmoplantar), and lichenoid skin reaction have been identified during post-approval use of TNF blockers.

Immune System Disorders: sarcoidosis

Neoplasms benign, malignant and unspecified (including cysts and polyps):Melanoma, Merkel cell carcinoma (neuroendocrine carcinoma of the skin) [see Warnings and Precautions (5.2)].

7 DRUG INTERACTIONS

7.1 Use with Anakinra, Abatacept, Rituximab, and Natalizumab

An increased risk of serious infections has been seen in clinical studies of other TNF-blocking agents used in combination with anakinra or abatacept, with no added benefit. Formal drug interaction studies have not been performed with rituximab or natalizumab. Because of the nature of the adverse events seen with these combinations with TNF blocker therapy, similar toxicities may also result from the use of CIMZIA in these combinations. There is not enough information to assess the safety and efficacy of such combination therapy. Therefore, the use of CIMZIA in combination with anakinra, abatacept, rituximab, or natalizumab is not recommended [see Warnings and Precautions (5.8)] .

7.2 Live Vaccines

Avoid use of live (including attenuated) vaccines during or immediately prior to initiation of therapy with CIMZIA [see Warnings and Precautions (5.10)] .

7.3 Laboratory Tests

Interference with certain coagulation assays has been detected in patients treated with CIMZIA. Certolizumab pegol may cause erroneously elevated activated partial thromboplastin time (aPTT) assay results in patients without coagulation abnormalities. This effect has been observed with the PTT-Lupus Anticoagulant (LA) test and Standard Target Activated Partial Thromboplastin time (STA-PTT) Automate tests from Diagnostica Stago, and the HemosIL APTT-SP liquid and HemosIL lyophilized silica tests from Instrumentation Laboratories. Other aPTT assays may be affected as well. Interference with thrombin time (TT) and prothrombin time (PT) assays has not been observed. There is no evidence that CIMZIA therapy has an effect on in vivocoagulation.

8 USE IN SPECIFIC POPULATIONS

8.1 Pregnancy

Pregnancy Exposure Registry

There is a pregnancy exposure registry that monitors pregnancy outcomes in women exposed to CIMZIA during pregnancy. For more information, healthcare providers or patients can contact:

MotherToBaby Pregnancy Studies conducted by the Organization of Teratology Information Specialists (OTIS). The OTIS AutoImmune Diseases Study at 1-877-311-8972 or visit http://mothertobaby.org/pregnancy-studies/.

Risk Summary

Limited data from an ongoing pregnancy exposure registry on use of CIMZIA in pregnant women are not sufficient to inform a risk of major birth defects or other adverse pregnancy outcomes. However, certolizumab pegol plasma concentrations obtained from two studies of CIMZIA use during the third trimester of pregnancy demonstrated that placental transfer of certolizumab pegol was negligible in most infants at birth, and low in other infants at birth (see Data) . There are risks to the mother and fetus associated with active rheumatoid arthritis or Crohn's disease. The theoretical risks of administration of live or live-attenuated vaccines to the infants exposed in uteroto CIMZIA should be weighed against the benefits of vaccinations (see Clinical Considerations) . No adverse developmental effects were observed in animal reproduction studies during which pregnant rats were administered intravenously a rodent anti-murine TNFα pegylated Fab' fragment (cTN3 PF) similar to certolizumab pegol during organogenesis at up to 2.4 times the recommended human dose of 400 mg every four weeks.

The background risk of major birth defects and miscarriage for the indicated population(s) are unknown. All pregnancies have a background risk of birth defect, loss, or other adverse outcomes. In the U.S. general population, the estimated background risks of major birth defects and miscarriage in clinically recognized pregnancies are 2 to 4% and 15 to 20%, respectively.

Clinical Considerations

Disease-Associated Maternal and/or Embryo/Fetal Risk

Published data suggest that the risk of adverse pregnancy outcomes in women with rheumatoid arthritis or Crohn's disease is correlated with maternal disease activity and that active disease increases the risk of adverse pregnancy outcomes, including fetal loss, preterm delivery (before 37 weeks of gestation), low birth weight (less than 2500 g) and small for gestational age birth.

Fetal/Neonatal Adverse Reaction

Due to its inhibition of TNFα, CIMZIA administered during pregnancy could affect immune responses in the in utero-exposed newborn and infant. The clinical significance of BLQ or low levels is unknown for in utero-exposed infants. Additional data available from one exposed infant suggest that CIMZIA may be eliminated at a slower rate in infants than in adults (see Data). The safety of administering live or live-attenuated vaccines in exposed infants is unknown.

Dosing During Pregnancy and the Postpartum Period

Based on a pharmacokinetic study in pregnant women with psoriasis or rheumatological diseases who were administered certolizumab pegol during pregnancy until at least 12 weeks postpartum, plasma certolizumab pegol concentrations throughout pregnancy were within the range observed in non-pregnant women with the same chronic inflammatory diseases. No dosage adjustment is required for pregnant women [see Clinical Pharmacology (12.3)].

Data

Human Data

A limited number of pregnancies have been reported in an ongoing pregnancy exposure registry. Due to the small number of CIMZIA-exposed pregnancies with known outcomes (n=217), no meaningful comparisons between the exposed group and control groups may be conducted to determine an association with CIMZIA and major birth defects or adverse pregnancy outcomes.

A multicenter clinical study was conducted in 16 women treated with CIMZIA at a maintenance dose of 200 mg every 2 weeks or 400 mg every 4 weeks during the third trimester of pregnancy for rheumatological diseases or Crohn's disease. The last dose of CIMZIA was given on average 11 days prior to delivery (range 1 to 27 days). Certolizumab pegol plasma concentrations were measured in samples from mothers and infants using an assay that can measure certolizumab pegol concentrations at or above 0.032 mcg/mL. Certolizumab pegol plasma concentrations measured in the mothers at delivery (range: 4.96 to 49.4 mcg/mL) were consistent with non-pregnant women's plasma concentrations in Study RA-I [see Clinical Studies (14.2)] . Certolizumab pegol plasma concentrations were not measurable in 13 out of 15 infants at birth. The concentration of certolizumab pegol in one infant was 0.0422 mcg/mL at birth (infant/mother plasma ratio of 0.09%). In a second infant, delivered by emergency Caesarean section, the concentration was 0.485 mcg/mL (infant/mother plasma ratio of 4.49%). At Week 4 and Week 8, all 15 infants had no measurable concentrations. Among 16 exposed infants, one serious adverse reaction was reported in a neonate who was treated empirically with intravenous antibiotics due to an increased white blood cell count; blood cultures were negative. The certolizumab pegol plasma concentrations for this infant were not measurable at birth, Week 4, or Week 8.

In another clinical study conducted in 10 pregnant women with Crohn´s disease treated with CIMZIA (400 mg every 4 weeks for every mother), certolizumab pegol concentrations were measured in maternal blood as well as in cord and infant blood at the day of birth with an assay that can measure concentrations at or above 0.41 mcg/mL. The last dose of CIMZIA was given on average 19 days prior to delivery (range 5 to 42 days). Plasma certolizumab pegol concentrations ranged from not measurable to 1.66 mcg/mL in cord blood and 1.58 mcg/mL in infant blood; and ranged from 1.87 to 59.57 mcg/mL in maternal blood. Plasma certolizumab pegol concentrations were lower (by at least 75%) in the infants than in mothers suggesting low placental transfer of certolizumab pegol. In one infant, the plasma certolizumab pegol concentration declined from 1.02 to 0.84 mcg/mL over 4 weeks suggesting that certolizumab pegol may be eliminated at a slower rate in infants than adults.

Animal Data

Because certolizumab pegol does not cross-react with mouse or rat TNFα, reproduction studies were performed in rats using a rodent anti-murine TNFα pegylated Fab' fragment (cTN3 PF) similar to certolizumab pegol. Animal reproduction studies have been performed in rats during organogenesis at intravenous doses up to 100 mg/kg (about 2.4 times the recommended human dose of 400 mg, based on the surface area) and have revealed no evidence of harm to the fetus due to cTN3 PF.

8.2 Lactation

Risk Summary

In a multicenter clinical study of 17 lactating women treated with CIMZIA at 200 mg every 2 weeks or 400 mg every 4 weeks, minimal certolizumab pegol concentrations were observed in breast milk. No serious adverse reactions were noted in the 17 infants in the study. There are no data on the effects on milk production. In a separate study, certolizumab pegol concentrations were not detected in the plasma of 9 breastfed infants at 4 weeks post-partum (see Data) . The developmental and health benefits of breastfeeding should be considered along with the mother's clinical need for CIMZIA and any potential adverse effects on the breastfed infant from CIMZIA or from the underlying maternal condition.

Data

A multicenter clinical study designed to evaluate breast milk was conducted in 17 lactating women who were at least 6 weeks post-partum and had received at least 3 consecutive doses of CIMZIA 200 mg every 2 weeks or 400 mg every 4 weeks for rheumatological disease or Crohn's disease. The effects of certolizumab pegol on milk production were not studied. The concentration of certolizumab pegol in breast milk was not measurable in 77 (56 %) of the 137 samples taken over the dosing periods using an assay that can measure certolizumab pegol concentrations at or above 0.032 mcg/mL. The median of the estimated average daily infant doses was 0.0035 mg/kg/day (range: 0 to 0.01 mg/kg/day). The percentage of the maternal dose (200 mg CIMZIA dosed once every 2 weeks), that reaches an infant ranged from 0.56% to 4.25% based on samples with measurable certolizumab pegol concentration. No serious adverse reactions were noted in the 17 breastfed infants in the study.

In a separate study, plasma certolizumab pegol concentrations were collected 4 weeks after birth in 9 breastfed infants whose mothers had been currently taking CIMZIA (regardless of being exclusively breastfed or not). Certolizumab pegol in infant plasma was not measurable i.e., below 0.032 mcg/mL.

8.4 Pediatric Use

The safety and effectiveness of CIMZIA for active polyarticular juvenile idiopathic arthritis has been established in pediatric patients 2 years of age and older. The use of CIMZIA in this age group is supported by evidence from adequate and well-controlled studies of CIMZIA in adults with RA, pharmacokinetic data from adults with RA and pediatric patients with JIA with active polyarthritis, and safety data from an open-label clinical study in 193 pediatric patients 2 to < 18 years of age with JIA with active polyarthritis. The observed pre-dose (trough) concentrations are generally comparable between adults with RA and pediatric patients with JIA with active polyarthritis [see Pharmacokinetics (12.3)].

The safety and effectiveness for CIMZIA in pediatric patients less than 2 years of age with pJIA have not been established.

The safety and effectiveness of CIMZIA have not been established in pediatric patients for other indications. CIMZIA was evaluated for the treatment of pediatric patients with moderately to severely active Crohn's disease. Effectiveness was not demonstrated in an open-label, randomized, parallel-group, multiple dose study for a period of up to 62 weeks in 99 subjects aged 6 to 17 years. The study was ended prematurely because of a high number of patient discontinuations.

Due to its inhibition of TNFα, CIMZIA administered during pregnancy could affect immune responses in the in utero-exposed newborn and infant [see Use in Specific Populations (8.1)].

8.5 Geriatric Use

Clinical studies of CIMZIA did not include sufficient numbers of patients aged 65 and over to determine whether they respond differently from younger subjects. Other reported clinical experience has not identified differences in responses between the elderly and younger adult patients. Population pharmacokinetic analyses of patients enrolled in CIMZIA clinical studies concluded that there was no apparent difference in drug concentration regardless of age. Because there is a higher incidence of infections in the elderly population in general, use caution when treating the elderly with CIMZIA [see Warnings and Precautions (5.1)] .

11 DESCRIPTION

Certolizumab pegol is a TNF blocker. CIMZIA is a recombinant, humanized antibody Fab' fragment, with specificity for human tumor necrosis factor alpha (TNFα), conjugated to an approximately 40kDa polyethylene glycol (PEG2MAL40K). The Fab' fragment is manufactured in E. coliand is subsequently subjected to purification and conjugation to PEG2MAL40K, to generate certolizumab pegol. The Fab' fragment is composed of a light chain with 214 amino acids and a heavy chain with 229 amino acids. The molecular weight of certolizumab pegol is approximately 91 kiloDaltons.

CIMZIA (certolizumab pegol) for injection is supplied as a sterile white, lyophilized powder in a single-dose vial for subcutaneous use. After reconstitution of the lyophilized powder with 1 mL Sterile Water for Injection, USP, the final concentration is 200 mg/mL with a deliverable volume of 1 mL (200 mg) and a pH of approximately 5.2. Each single-dose vial provides 200 mg certolizumab pegol, lactic acid (0.9 mg), polysorbate (0.1 mg), and sucrose (100 mg).

CIMZIA (certolizumab pegol) injection is supplied as a sterile, clear to opalescent, colorless to yellow solution that may contain particulates in a single-dose prefilled syringe for subcutaneous use. Each prefilled syringe delivers 1 mL of solution containing 200 mg certolizumab pegol, sodium acetate (1.36 mg), sodium chloride (7.31 mg), and Water for Injection, USP.

12 CLINICAL PHARMACOLOGY

12.1 Mechanism of Action

Certolizumab pegol binds to human TNFα with a KD of 90pM. TNFα is a key pro-inflammatory cytokine with a central role in inflammatory processes. Certolizumab pegol selectively neutralizes TNFα (IC90of 4 ng/mL for inhibition of human TNFα in the in vitroL929 murine fibrosarcoma cytotoxicity assay) but does not neutralize lymphotoxin α (TNFβ). Certolizumab pegol cross-reacts poorly with TNF from rodents and rabbits, therefore in vivoefficacy was evaluated using animal models in which human TNFα was the physiologically active molecule.

Certolizumab pegol was shown to neutralize membrane-associated and soluble human TNFα in a dose-dependent manner. Incubation of monocytes with certolizumab pegol resulted in a dose-dependent inhibition of LPS-induced TNFα and IL-1β production in human monocytes.

Certolizumab pegol does not contain a fragment crystallizable (Fc) region, which is normally present in a complete antibody, and therefore does not fix complement or cause antibody-dependent cell-mediated cytotoxicity in vitro. It does not induce apoptosis in vitroin human peripheral blood-derived monocytes or lymphocytes, nor does certolizumab pegol induce neutrophil degranulation.

A tissue reactivity study was carried out ex vivoto evaluate potential cross-reactivity of certolizumab pegol with cryosections of normal human tissues. Certolizumab pegol showed no reactivity with a designated standard panel of normal human tissues.

12.2 Pharmacodynamics

Biological activities ascribed to TNFα include the upregulation of cellular adhesion molecules and chemokines, upregulation of major histocompatibility complex (MHC) class I and class II molecules, and direct leukocyte activation. TNFα stimulates the production of downstream inflammatory mediators, including interleukin-1, prostaglandins, platelet activating factor, and nitric oxide. Elevated levels of TNFα have been implicated in the pathology of Crohn's disease and rheumatoid arthritis. Certolizumab pegol binds to TNFα, inhibiting its role as a key mediator of inflammation. TNFα is strongly expressed in the bowel wall in areas involved by Crohn's disease and fecal concentrations of TNFα in patients with Crohn's disease have been shown to reflect clinical severity of the disease. After treatment with certolizumab pegol, patients with Crohn's disease demonstrated a decrease in the levels of C-reactive protein (CRP). Increased TNFα levels are found in the synovial fluid of rheumatoid arthritis patients and play an important role in the joint destruction that is a hallmark of this disease.

12.3 Pharmacokinetics

Absorption

A total of 126 healthy subjects received doses of up to 800 mg certolizumab pegol subcutaneously (sc) and up to 10 mg/kg intravenously (IV) in four pharmacokinetic studies. Data from these studies demonstrate that single intravenous and subcutaneous doses of certolizumab pegol have predictable dose-related plasma concentrations with a linear relationship between the dose administered and the maximum plasma concentration (Cmax), and the Area Under the certolizumab pegol plasma concentration versus time Curve (AUC). A mean Cmaxof approximately 43 to 49 mcg/mL occurred at Week 5 during the initial loading dose period using the recommended dose regimen for the treatment of patients with rheumatoid arthritis (400 mg sc at Weeks 0, 2 and 4 followed by 200 mg every other week).

Certolizumab pegol plasma concentrations were broadly dose-proportional and pharmacokinetics observed in patients with rheumatoid arthritis, Crohn's disease, and plaque psoriasis were consistent with those seen in healthy subjects.

Following subcutaneous administration, peak plasma concentrations of certolizumab pegol were attained between 54 and 171 hours post-injection. Certolizumab pegol has bioavailability (F) of approximately 80% (ranging from 76% to 88%) following subcutaneous administration compared to intravenous administration.

In pediatric patients with JIA with active polyarthritis, mean peak plasma concentrations, measured 1 week following loading dose and maintenance dose were 58.8 µg/ml and 41.8 µg/ml, respectively. Similar peak plasma concentrations were observed across the different body weight groups (10 kg to less than 20 kg, 20 kg to less than 40 kg, and greater than or equal to 40 kg).

Distribution

The steady state volume of distribution (Vss) was estimated as 4.7 to 8 L in the population pharmacokinetic analysis for adult patients with Crohn's disease, patients with rheumatoid arthritis, and adult patients with plaque psoriasis.

The volume of distribution in pediatric patients with JIA with active polyarthritis was dependent on body size.

Metabolism

The metabolism of certolizumab pegol has not been studied in human subjects. Data from animals indicate that once cleaved from the Fab' fragment the PEG moiety is mainly excreted in urine without further metabolism.

Elimination

PEGylation, the covalent attachment of PEG polymers to peptides, delays the metabolism and elimination of these entities from the circulation by a variety of mechanisms, including decreased renal clearance, proteolysis, and immunogenicity. Accordingly, certolizumab pegol is an antibody Fab' fragment conjugated with PEG in order to extend the terminal plasma elimination half-life (t1/2) of the Fab'. The terminal elimination phase half-life (t1/2) was approximately 14 days for all doses tested. The clearance following IV administration to healthy subjects ranged from 9.21 mL/h to 14.38 mL/h. The clearance following sc dosing was estimated 17 mL/h in the Crohn's disease population PK analysis with an inter-subject variability of 38% (CV) and an inter-occasion variability of 16%. Similarly, the clearance following sc dosing was estimated as 21.0 mL/h in the RA population PK analysis, with an inter-subject variability of 30.8% (%CV) and inter-occasion variability 22.0%. The clearance following subcutaneous dosing in patients with plaque psoriasis was 14 mL/h with an inter-subject variability of 22.2% (CV). The route of elimination of certolizumab pegol has not been studied in human subjects. Studies in animals indicate that the major route of elimination of the PEG component is via urinary excretion.

In pediatric patients with JIA with active polyarthritis, clearance was body weight dependent, and t1/2was similar to adult indications.

Specific Populations

Population pharmacokinetic analysis was conducted on data from adult patients with rheumatoid arthritis and adult patients with Crohn's disease, to evaluate the effect of age, race, sex, concomitant medication (NSAIDs, Cyclooxygenase-2 (COX-2) inhibitors, DMARDs including methotrexate), creatinine clearance and presence of anti-certolizumab antibodies on pharmacokinetics of certolizumab pegol. A population pharmacokinetic analysis was also conducted on data from patients with plaque psoriasis to evaluate the effect of age, sex, body weight, and presence of anti-certolizumab pegol antibodies. Only bodyweight and presence of anti-certolizumab antibodies significantly affected certolizumab pegol pharmacokinetics. Pharmacokinetic exposure was inversely related to body weight but pharmacodynamic exposure-response analysis showed that no additional therapeutic benefit would be expected from a weight-adjusted dose regimen. When assessed using the previous ELISA method, the presence of anti-certolizumab antibodies was associated with a ≥ 3 to 4 fold increase in clearance.

Geriatric Patients:Pharmacokinetics of certolizumab pegol was not different in elderly compared to young adults (≥18 years old).

Pregnant Patients

In a pharmacokinetic study, 21 women were treated with CIMZIA subcutaneously during pregnancy and through at least 12 weeks postpartum. Based on population pharmacokinetic analysis, median plasma pre-dose concentrations and Cmaxof certolizumab pegol were lower (by up to 36% and 19%, respectively) during pregnancy compared to postpartum; however, the concentrations during pregnancy were within the range of observed concentrations in non-pregnant adult patients in clinical studies of rheumatoid arthritis, ankylosing spondylitis, non-radiographic axial spondyloarthritis, and plaque psoriasis.

Pediatric Patients:

In the JIA with active polyarthritis study (NCT01550003), the mean trough plasma concentrations at Week 12 (steady-state) were 31.8 µg/mL, 27.9 µg/mL, and 36.8 µg/mL for patients weighing 10 to <20 kg, 20 to <40 kg, and ≥40 kg, respectively. Population pharmacokinetic analyses showed that plasma concentrations in pediatric patients with JIA with active polyarthritis are in the same range as observed in adult patients with RA receiving a 200 mg Q2W maintenance dose.

Similar to the adult data, body weight and anti-certolizumab antibodies titers affected certolizumab pegol pharmacokinetics, where higher body weights and presence of anti-certolizumab antibodies was associated with lower exposures. There was no observed impact from the use of concomitant methotrexate on certolizumab pegol plasma concentrations.

Racial or Ethnic Groups:A specific clinical study showed no difference in pharmacokinetics between Caucasian and Japanese subjects.

Male and Female Patients:Pharmacokinetics of certolizumab pegol was similar in male and female subjects in both adult and pediatric patients.

Patients with Renal Impairment:Specific clinical studies have not been performed to assess the effect of renal impairment on the pharmacokinetics of CIMZIA. The pharmacokinetics of the PEG (polyethylene glycol) fraction of certolizumab pegol is expected to be dependent on renal function but has not been assessed in renal impairment. There are insufficient data to provide a dosing recommendation in moderate and severe renal impairment.

Drug Interaction Studies

Methotrexate pharmacokinetics is not altered by concomitant administration with CIMZIA in patients with rheumatoid arthritis. The effect of methotrexate on CIMZIA pharmacokinetics was not studied. However, methotrexate-treated patients have lower incidence of antibodies to CIMZIA. Thus, therapeutic plasma levels are more likely to be sustained when CIMZIA is administered with methotrexate in patients with rheumatoid arthritis.

Formal drug-drug interaction studies have not been conducted with CIMZIA upon concomitant administration with corticosteroids, nonsteroidal anti-inflammatory drugs, analgesics or immunosuppressants.

13 NONCLINICAL TOXICOLOGY

13.1 Carcinogenesis, Mutagenesis, and Impairment of Fertility

Long-term animal studies of CIMZIA have not been conducted to assess its carcinogenic potential. Certolizumab pegol was not genotoxic in the Ames test, the human peripheral blood lymphocytes chromosomal aberration assay, or the mouse bone marrow micronucleus assay.

Since certolizumab pegol does not cross-react with mouse or rat TNFα, reproduction studies were performed in rats using a rodent anti-murine TNFα pegylated Fab fragment (cTN3 PF), similar to certolizumab pegol. The cTN3 PF had no effects on the fertility and general reproductive performance of male and female rats at intravenous doses up 100 mg/kg, administered twice weekly.

14 CLINICAL STUDIES

14.1 Crohn's Disease

The efficacy and safety of CIMZIA were assessed in two double-blind, randomized, placebo-controlled studies in patients aged 18 years and older with moderately to severely active Crohn's disease, as defined by a Crohn's Disease Activity Index (CDAI) of 220 to 450 points, inclusive. CIMZIA was administered subcutaneously at a dose of 400 mg in both studies. Stable concomitant medications for Crohn's disease were permitted.

Study CD1

Study CD1 was a randomized placebo-controlled study in 662 patients with active Crohn's disease. CIMZIA or placebo was administered at Weeks 0, 2, and 4 and then every four weeks to Week 24. Assessments were done at Weeks 6 and 26. Clinical response was defined as at least a 100-point reduction in CDAI score compared to baseline, and clinical remission was defined as an absolute CDAI score of 150 points or lower.

The results for Study CD1 are provided in Table 3. At Week 6, the proportion of clinical responders was statistically significantly greater for CIMZIA-treated patients compared to controls. The difference in clinical remission rates was not statistically significant at Week 6. The difference in the proportion of patients who were in clinical response at both Weeks 6 and 26 was also statistically significant, demonstrating maintenance of clinical response.

Table 3: Study CD1 – Clinical Response and Remission, Overall Study Population
Timepoint | % Response or Remission (95% CI)
Timepoint | Placebo (N = 328) | CIMZIA 400 mg (N = 331)
Week 6
Clinical Response [Clinical response is defined as decrease in CDAI of at least 100 points, and clinical remission is defined as CDAI ≤ 150 points] | 27%(22%, 32%) | 35%(30%, 40%) [p-value < 0.05 logistic regression test]
Clinical Remission | 17%(13%, 22%) | 22%(17%, 26%)
Week 26
Clinical Response | 27%(22%, 31%) | 37%(32%, 42%)
Clinical Remission | 18%(14%, 22%) | 29%(25%, 34%)
Both Weeks 6 & 26
Clinical Response | 16%(12%, 20%) | 23%(18%, 28%)
Clinical Remission | 10%(7%, 13%) | 14%(11%, 18%)

Study CD2

Study CD2 was a randomized treatment-withdrawal study in patients with active Crohn's disease. All patients who entered the study were dosed initially with CIMZIA 400 mg at Weeks 0, 2, and 4 and then assessed for clinical response at Week 6 (as defined by at least a 100-point reduction in CDAI score). At Week 6, a group of 428 clinical responders was randomized to receive either CIMZIA 400 mg or placebo, every four weeks starting at Week 8, as maintenance therapy through Week 24. Non-responders at Week 6 were withdrawn from the study. Final evaluation was based on the CDAI score at Week 26. Patients who withdrew or who received rescue therapy were considered not to be in clinical response. Three randomized responders received no study injections, and were excluded from the ITT analysis.

The results for clinical response and remission are shown in Table 4. At Week 26, a statistically significantly greater proportion of Week 6 responders were in clinical response and in clinical remission in the CIMZIA-treated group compared to the group treated with placebo.

Table 4: Study CD2 - Clinical Response and Clinical Remission
 | % Response or Remission (95% CI)
 | CIMZIA 400 mg ×3 + Placebo N = 210 | CIMZIA 400 mg N = 215
Week 26
Clinical Response [Clinical response is defined as decrease in CDAI of at least 100 points, and clinical remission is defined as CDAI ≤ 150 points] | 36%(30%, 43%) | 63%(56%, 69%) [p < 0.05]
Clinical Remission | 29%(22%, 35%) | 48%(41%, 55%)

Baseline use of immunosuppressants or corticosteroids had no impact on the clinical response to CIMZIA.

14.2 Rheumatoid Arthritis

The efficacy and safety of CIMZIA were assessed in four randomized, placebo-controlled, double-blind studies (RA-I, RA-II, RA-III, and RA-IV) in patients ≥ 18 years of age with moderately to severely active rheumatoid arthritis diagnosed according to the American College of Rheumatology (ACR) criteria. Patients had ≥ 9 swollen and tender joints and had active RA for at least 6 months prior to baseline. CIMZIA was administered subcutaneously in combination with MTX at stable doses of at least 10 mg weekly in Studies RA-I, RA-II, and RA-III. CIMZIA was administered as monotherapy in Study RA-IV.

Study RA-I and Study RA-II evaluated patients who had received MTX for at least 6 months prior to study medication, but had an incomplete response to MTX alone. Patients were treated with a loading dose of 400 mg at Weeks 0, 2 and 4 (for both treatment arms) or placebo followed by either 200 mg or 400 mg of CIMZIA or placebo every other week, in combination with MTX for 52 weeks in Study RA-I and for 24 weeks in Study RA-II. Patients were evaluated for signs and symptoms and structural damage using the ACR20 response at Week 24 (RA-I and RA-II) and modified Total Sharp Score (mTSS) at Week 52 (RA-I). The open-label extension follow-up study enrolled 846 patients who received 400 mg of CIMZIA every other week.

Study RA-III evaluated 247 patients who had active disease despite receiving MTX for at least 6 months prior to study enrollment. Patients received 400 mg of CIMZIA every four weeks for 24 weeks without a prior loading dose. Patients were evaluated for signs and symptoms of RA using the ACR20 at Week 24.

Study RA-IV (monotherapy) evaluated 220 patients who had failed at least one DMARD use prior to receiving CIMZIA. Patients were treated with CIMZIA 400 mg or placebo every 4 weeks for 24 weeks. Patients were evaluated for signs and symptoms of active RA using the ACR20 at Week 24.

Clinical Response

The percent of CIMZIA-treated patients achieving ACR20, 50, and 70 responses in Studies RA-I and RA-IV are shown in Table 5. CIMZIA-treated patients had higher ACR20, 50 and 70 response rates at 6 months compared to placebo-treated patients. The results in study RA-II (619 patients) were similar to the results in RA-I at Week 24. The results in study RA-III (247 patients) were similar to those seen in study RA-IV. Over the one-year Study RA-I, 13% of CIMZIA-treated patients achieved a major clinical response, defined as achieving an ACR70 response over a continuous 6-month period, compared to 1% of placebo-treated patients.

Table 5: ACR Responses in Studies RA-I, and RA-IV (Percent of Patients)
 | Study RA-I Methotrexate Combination (24 and 52 weeks) |  |  | Study RA-IV Monotherapy (24 weeks)
Response | Placebo + MTX | CIMZIA [CIMZIA administered every 2 weeks preceded by a loading dose of 400 mg at Weeks 0, 2 and 4] 200 mg + MTX q 2 weeks | CIMZIA 200 mg + MTX - Placebo + MTX | Placebo | CIMZIA [CIMZIA administered every 4 weeks not preceded by a loading dose regimen] 400 mg q 4 weeks | CIMZIA 400 mg - Placebo
Response | N=199 | N=393 | (95% CI) [95% Confidence Intervals constructed using the large sample approximation to the Normal Distribution.] | N=109 | N=111 | (95% CI)
ACR20
Week 24 | 14% | 59% | 45% (38%, 52%) | 9% | 46% | 36% (25%, 47%)
Week 52 | 13% | 53% | 40% (33%, 47%) | N/A | N/A
ACR50
Week 24 | 8% | 37% | 30% (24%, 36%) | 4% | 23% | 19% (10%, 28%)
Week 52 | 8% | 38% | 30% (24%, 37%) | N/A | N/A
ACR70
Week 24 | 3% | 21% | 18% (14%, 23%) | 0% | 6% | 6% (1%, 10%)
Week 52 | 4% | 21% | 18% (13%, 22%) | N/A | N/A
Major Clinical Response [Major clinical response is defined as achieving ACR70 response over a continuous 6-month period] | 1% | 13% | 12% (8%, 15%)

Table 6: Components of ACR Response in Studies RA-I and RA-IV
 | Study RA-I |  |  |  | Study RA-IV
Parameter [For Study RA-I, median is presented. For Study RA-IV, mean (SD) is presented except for CRP which presents geometric mean] | Placebo + MTX N=199 |  | CIMZIA [CIMZIA administered every 2 weeks preceded by a loading dose of 400 mg at Weeks 0, 2 and 4] 200 mg + MTX q 2 weeks N=393 |  | Placebo N=109 |  | CIMZIA [CIMZIA administered every 4 weeks not preceded by a loading dose regimen] 400 mg q 4 weeks Monotherapy N=111
 | Baseline | Week 24 | Baseline | Week 24 | Baseline | Week 24 | Baseline | Week 24
Number of tender joints (0-68) | 28 | 27 | 29 | 9 | 28 (12.5) | 24 (15.4) | 30 (13.7) | 16 (15.8)
Number of swollen joints (0-66) | 20 | 19 | 20 | 4 | 20 (9.3) | 16 (12.5) | 21 (10.1) | 12 (11.2)
Physician global assessment [Study RA-I - Visual Analog Scale: 0 = best, 100 = worst. Study RA-IV - Five Point Scale: 1 = best, 5 = worst] | 66 | 56 | 65 | 25 | 4 (0.6) | 3 (1.0) | 4 (0.7) | 3 (1.1)
Patient global assessment | 67 | 60 | 64 | 32 | 3 (0.8) | 3 (1.0) | 3 (0.8) | 3 (1.0)
Pain [Patient Assessment of Arthritis Pain . Visual Analog Scale: 0 = best, 100 = worst] | 65 | 60 | 65 | 32 | 55 (20.8) | 60 (26.7) | 58 (21.9) | 39 (29.6)
Disability index (HAQ) [Health Assessment Questionnaire Disability Index; 0 = best, 3 = worst, measures the patient's ability to perform the following: dress/groom, arise, eat, walk, reach, grip, maintain hygiene, and maintain daily activity All values are last observation carried forward.] | 1.75 | 1.63 | 1.75 | 1.00 | 1.55 (0.65) | 1.62 (0.68) | 1.43 (0.63) | 1.04 (0.74)
CRP (mg/L) | 16.0 | 14.0 | 16.0 | 4.0 | 11.3 | 13.5 | 11.6 | 6.4

The percent of patients achieving ACR20 responses by visit for Study RA-I is shown in Figure 1. Among patients receiving CIMZIA, clinical responses were seen in some patients within one to two weeks after initiation of therapy.

Figure 1 Study RA-I ACR20 Response Over 52 Weeks [The same patients may not have responded at each time point]

Radiographic Response

In Study RA-I, inhibition of progression of structural damage was assessed radiographically and expressed as the change in modified Total Sharp Score (mTSS) and its components, the Erosion Score (ES) and Joint Space Narrowing (JSN) score, at Week 52, compared to baseline. CIMZIA inhibited the progression of structural damage compared to placebo plus MTX after 12 months of treatment as shown in Table 7. In the placebo group, 52% of patients experienced no radiographic progression (mTSS ≤0.0) at Week 52 compared to 69% in the CIMZIA 200 mg every other week treatment group. Study RA-II showed similar results at Week 24.

Table 7: Radiographic Changes at 6 and 12 months in Study RA-I
 | Placebo + MTX N=199 Mean (SD) | CIMZIA 200 mg + MTX N=393 Mean (SD) | CIMZIA 200 mg + MTX – Placebo + MTX Mean Difference
mTSS
Baseline | 40 (45) | 38 (49) | --
Week 24 | 1.3 (3.8) | 0.2 (3.2) | -1.1
Week 52 | 2.8 (7.8) | 0.4 (5.7) | -2.4
Erosion Score
Baseline | 14 (21) | 15 (24) | --
Week 24 | 0.7 (2.1) | 0.0 (1.5) | -0.7
Week 52 | 1.5 (4.3) | 0.1 (2.5) | -1.4
JSN Score
Baseline | 25 (27) | 24 (28) | --
Week 24 | 0.7 (2.4) | 0.2 (2.5) | -0.5
Week 52 | 1.4 (5.0) | 0.4 (4.2) | -1.0
An ANCOVA was fitted to the ranked change from baseline for each measure with region and treatment as factors and rank baseline as a covariate.

Physical Function Response

In studies RA-I, RA-II, RA-III, and RA-IV, CIMZIA-treated patients achieved greater improvements from baseline than placebo-treated patients in physical function as assessed by the Health Assessment Questionnaire – Disability Index (HAQ-DI) at Week 24 (RA-II, RA-III and RA-IV) and at Week 52 (RA-I).

14.3 Polyarticular Juvenile Idiopathic Arthritis

The efficacy of CIMZIA in pediatric patients with pJIA is based on pharmacokinetic exposure and extrapolation of the established efficacy of CIMZIA in RA patients.

The efficacy of CIMZIA was also assessed in a multi-center, open-label study NCT01550003 in 193 patients 2 to 17 years of age with JIA with active polyarthritis with an inadequate response or intolerance to at least 1 DMARD (nonbiologic or biologic). Of those, 105 received the recommended dose. The patients had the following subtypes of JIA: polyarthritis rheumatoid factor-positive (20.0%), polyarthritis rheumatoid factor-negative (44.8%), extended oligoarthritis (13.3%), juvenile psoriatic arthritis (4.8%), and enthesitis-related arthritis (19.0%). Patients could be on stable methotrexate, glucocorticoids, and/or NSAIDs. Efficacy was assessed as secondary endpoints through Week 24. The efficacy was generally consistent with responses in patients with RA.

14.4 Psoriatic Arthritis

The efficacy and safety of CIMZIA were assessed in a multi-center, randomized, double-blind, placebo controlled trial (PsA001) in 409 patients aged 18 years and older with active psoriatic arthritis despite DMARD therapy. Patients in this study had ≥ 3 swollen and tender joints and adult-onset PsA of at least 6 months' duration as defined by the Classification Criteria for Psoriatic Arthritis (CASPAR) criteria, and increased acute phase reactants. Patients had failed one or more DMARDs. Previous treatment with one anti-TNF biologic therapy was allowed, and 20% of patients had prior anti-TNF biologic exposure. Patients receiving concomitant NSAIDs and conventional DMARDs were 73% and 70 % respectively.

Patients received a loading dose of CIMZIA 400 mg at Weeks 0, 2 and 4 (for both treatment arms) or placebo followed by either CIMZIA 200 mg every other week or CIMZIA 400 mg every 4 weeks or placebo every other week. Patients were evaluated for signs and symptoms and structural damage using the ACR20 response at Week 12 and modified Total Sharp Score (mTSS) at Week 24.

Clinical Response

The percentage of CIMZIA-treated patients achieving ACR20, 50 and 70 responses in study PsA001 are shown in Table 8. ACR20 response rates at weeks 12 and 24 were higher for each CIMZIA dose group relative to placebo (95% confidence intervals for CIMZIA 200 mg minus placebo at weeks 12 and 24 of (23%, 45%) and (30%, 51%), respectively and 95% confidence intervals for CIMZIA 400 mg minus placebo at weeks 12 and 24 of (17%, 39%) and (22%, 44%), respectively). The results of the components of the ACR response criteria are shown in Table 9.

Patients with enthesitis at baseline were evaluated for mean improvement in Leeds Enthesitis Index (LEI). CIMZIA-treated patients receiving either 200 mg every 2 weeks or 400 mg every 4 weeks showed a reduction in enthesitis of 1.8 and 1.7, respectively as compared with a reduction in placebo-treated patients of 0.9 at week 12. Similar results were observed for this endpoint at week 24. Treatment with CIMZIA resulted in improvement in skin manifestations in patients with PsA.

Table 8: ACR Responses in Study PsA001 (Percent of Patients)
Response [Results are from the randomized set. Non-responder Imputation (NRI) is used for patients who escaped therapy or had missing data.] | Placebo | CIMZIA [CIMZIA administered every 2 weeks preceded by a loading dose of 400 mg at Weeks 0, 2 and 4] 200 mg Q2W | CIMZIA [CIMZIA administered every 4 weeks preceded by a loading dose of 400 mg at Weeks 0, 2 and 4] 400 mg Q4W
 | N=136 | N=138 | N=135
ACR20
Week 12 | 24% | 58% | 52%
Week 24 | 24% | 64% | 56%
ACR50
Week 12 | 11% | 36% | 33%
Week 24 | 13% | 44% | 40%
ACR70
Week 12 | 3% | 25% | 13%
Week 24 | 4% | 28% | 24%

Table 9: Components of ACR Response in Study PsA001
Parameter | Placebo [Results are from the entire placebo group] N=136 |  | CIMZIA [CIMZIA administered every 2 weeks preceded by a loading dose of 400 mg at Weeks 0, 2 and 4] 200 mg Q2W N=138 |  | CIMZIA [CIMZIA administered every 4 weeks preceded by a loading dose of 400 mg at Weeks 0, 2 and 4] 400 mg Q4W N=135
 | Baseline | Week 12 | Baseline | Week 12 | Baseline | Week 12
Number of tender joints (0-68) [Last Observation Carried Forward is used for missing data, early withdrawals or placebo escape] | 20 | 17 | 22 | 11 | 20 | 11
Number of swollen joints (0-66) | 10 | 9 | 11 | 4 | 11 | 5
Physician global assessment , [Patient and Physician Global Assessment of Disease Activity, VAS 0=best 100= worst] | 59 | 44 | 57 | 25 | 58 | 29
Patient global assessment , | 57 | 50 | 60 | 33 | 60 | 40
Pain , [The Patient Assessment of Arthritis Pain, VAS 0=no pain and 100= most severe pain] | 60 | 50 | 60 | 33 | 61 | 39
Disability index (HAQ) , [The HAQ-DI, 4 point scale 0=without difficulty and 3=unable to do] | 1.30 | 1.15 | 1.33 | 0.87 | 1.29 | 0.90
CRP (mg/L) | 18.56 | 14.75 | 15.36 | 5.67 | 13.71 | 6.34
All values presented represent the mean
Results are from the randomized set (either with imputation or observed case)

The percent of patients achieving ACR20 responses by visit for PsA001 is shown in Figure 2.

Figure 2: Study PsA001-ACR20 Response Over 24 Weeks [The same patients may not have responded at each time point.]

Randomized Set. Non-responder imputation used for patients with missing data or those who escaped therapy.

Radiographic Response

In study PsA001, inhibition of progression of structural damage was assessed radiographically and expressed as the change in modified total Sharp score (mTSS) and its components, the Erosion Score (ES) and Joint Space Narrowing score (JSN) at week 24, compared to baseline. The mTSS score was modified for psoriatic arthritis by addition of hand distal interphalangeal (DIP) joints.

Patients treated with CIMZIA 200 mg every other week demonstrated greater reduction in radiographic progression compared with placebo-treated patients at Week 24 as measured by change from baseline in total modified mTSS Score (estimated mean score was 0.18 in the placebo group compared with -0.02 in the CIMZIA 200 mg group; 95% CI for the difference was (-0.38, -0.04)). Patients treated with CIMZIA 400 mg every four weeks did not demonstrate greater inhibition of radiographic progression compared with placebo-treated patients at Week 24.

Physical Function Response

In Study PsA001, CIMZIA-treated patients showed improvement in physical function as assessed by the Health Assessment Questionnaire – Disability Index (HAQ-DI) at Week 24 as compared to placebo (estimated mean change from baseline was 0.19 in the placebo group compared with 0.54 in the CIMZIA 200 mg group; 95% CI for the difference was (-0.47, -0.22) and 0.46 in the CIMZIA 400 mg group; 95% CI for the difference was (-0.39, -0.14)).

14.5 Ankylosing Spondylitis

The efficacy and safety of CIMZIA were assessed in one multicenter, randomized, double-blind, placebo-controlled study (AS-1) in 325 patients ≥18 years of age with adult-onset active axial spondyloarthritis for at least 3 months. The majority of patients in the study had active AS.

Patients had active disease as defined by the Bath Ankylosing Spondylitis Disease Activity Index (BASDAI) ≥4, and spinal pain ≥4 on a 0 to 10 Numerical Rating Scale (NRS). Patients must have been intolerant to or had an inadequate response to at least one NSAID. Patients were treated with a loading dose of CIMZIA 400 mg at Weeks 0, 2 and 4 (for both treatment arms) or placebo followed by either 200 mg of CIMZIA every 2 weeks or 400 mg of CIMZIA every 4 weeks or placebo. Concomitant NSAIDs were received by 91% of the AS patients. The primary efficacy variable was the proportion of patients achieving an ASAS20 response at Week 12.

Clinical Response

In study AS-1, at Week 12, a greater proportion of AS patients treated with CIMZIA 200 mg every 2 weeks or 400 mg every 4 weeks achieved ASAS 20 response compared to AS patients treated with placebo (Table 10). Responses were similar in patients receiving CIMZIA 200 mg every 2 weeks and CIMZIA 400 mg every 4 weeks. The results of the components of the ASAS response criteria and other measures of disease activity are shown in Table 11.

Table 10: ASAS Responses in AS patients at Weeks 12 and 24 in study AS-1
Parameters | Placebo N=57 | CIMZIA [CIMZIA administered every 2 weeks preceded by a loading dose of 400 mg at Weeks 0, 2 and 4] 200 mg every 2 weeks N=65 | CIMZIA [CIMZIA administered every 4 weeks preceded by a loading dose of 400 mg at Weeks 0, 2 and 4] 400 mg every 4 weeks N=56
ASAS20
Week 12 | 37% | 57% | 64%
Week 24 | 33% | 68% | 70%
ASAS40
Week 12 | 19% | 40% | 50%
Week 24 | 16% | 48% | 59%
All percents reflect the proportion of patients who responded in the full analysis set

Table 11: Components of the ASAS response criteria and other measures of disease activity in AS patients at baseline and Week 12 in study AS-1
 | Placebo N=57 |  | CIMZIA [CIMZIA administered every 2 weeks preceded by a loading dose of 400 mg at Weeks 0, 2 and 4] 200 mg every 2 weeks N=65 |  | CIMZIA [CIMZIA administered every 4 weeks preceded by a loading dose of 400 mg at Weeks 0, 2 and 4] 400 mg every 4 weeks N=56
 | Baseline | Week 12 | Baseline | Week 12 | Baseline | Week 12
ASAS20 response criteria
-Patient Global Assessment (0-10) | 6.9 | 5.6 | 7.3 | 4.2 | 6.8 | 3.8
-Total spinal pain (0-10) | 7.3 | 5.8 | 7.0 | 4.3 | 6.9 | 4.0
-BASFI (0-10) [BASFI is Bath Ankylosing Spondylitis Functional Index] | 6.0 | 5.2 | 5.6 | 3.8 | 5.7 | 3.8
-Inflammation (0-10) | 6.7 | 5.5 | 6.7 | 3.8 | 6.4 | 3.4
BASDAI (0-10) [BASDAI is Bath Ankylosing Spondylitis Disease Activity Index] | 6.4 | 5.4 | 6.5 | 4.0 | 6.2 | 3.7
BASMI [BASMI is Bath Ankylosing Spondylitis Metrology Index] | 4.8 | 4.4 | 4.2 | 3.6 | 4.3 | 3.9
All values presented represent the mean in the full analysis set

The percent of AS patients achieving ASAS20 responses by visit for Study AS001 is shown in Figure 3. Among patients receiving CIMZIA, clinical responses were seen in some AS patients within one to two weeks after initiation of therapy.

Figure 3: Study AS-1: ASAS20 response over 24 weeks in AS patients *

14.6 Non-radiographic Axial Spondyloarthritis

The efficacy and safety of CIMZIA were assessed in a multicenter, randomized, double-blind, placebo-controlled study (nr-axSpA-1) (NCT02552212) in 317 subjects ≥18 years of age with adult-onset active axial spondyloarthritis for at least 12 months. Patients must have had objective signs of inflammation indicated by C-reactive protein (CRP) levels above the upper limit of normal and/or sacroiliitis on magnetic resonance imaging (MRI), indicative of inflammatory disease [positive CRP (> ULN) and/or positive MRI], but without definitive radiographic evidence of structural damage on sacroiliac joints. Patients had active disease as defined by the Bath Ankylosing Spondylitis Disease Activity Index (BASDAI) ≥4, and spinal pain ≥4 on a 0 to 10 Numerical Rating Scale (NRS). Patients must have been intolerant to or had an inadequate response to at least two NSAIDs. Patients were treated with a loading dose of CIMZIA 400 mg at Weeks 0, 2 and 4 or placebo followed by 200 mg of CIMZIA every 2 weeks or placebo. Utilization and dose adjustment of concomitant medications (including NSAIDs, DMARDs, corticosteroids, opioids) were permitted at any time. Patients were allowed to transition to use of open-label CIMZIA at any time at the discretion of the investigator. However, no patients transitioned before Week 12. The primary endpoint was the proportion of patients achieving an Ankylosing Spondylitis Disease Activity Score-Major Improvement (ASDAS-MI) response at Week 52. The ASDAS is a composite weighted scoring system that assesses disease activity, including patient-reported outcomes and CRP levels. A response in ASDAS-Major Improvement (MI) is indicated by a change from baseline of ≥2.0 in the ASDAS and/or reaching the lowest possible ASDAS value.

Clinical Response

In study nr-axSpA-1, at Week 52, a greater proportion of nr-axSpA patients treated with CIMZIA had ASDAS-MI response compared to patients treated with placebo. At both Weeks 12 and 52, ASAS40 responses were greater for patients treated with CIMZIA compared to patients treated with placebo (Table 12). The components of the ASDAS-MI and ASAS response criteria are shown in Table 13.

Table 12: Clinical Responses in nr-axSpA patients at Weeks 12 and 52 in study nr-axSpA-1
Parameters | Placebo | CIMZIA [CIMZIA administered every 2 weeks preceded by a loading dose of 400 mg at Weeks 0, 2, and 4 All percents reflect the proportion of patients who were responders and remained in the study and on randomized treatment in the full analysis set. Patients who initiated open-label CIMZIA, or discontinued randomized treatment and remained in the study, or were missing Week 52 visit data were imputed as non-responders.] 200 mg every 2 weeks | CIMZIA 200 mg versus Placebo Odds ratio (95% CI)
 | N=158 | N=159 | CIMZIA 200 mg versus Placebo Odds ratio (95% CI)
ASDAS-MI
Week 52 | 7% | 47% | 15.2 (7.3 , 31.6)
ASAS-40
Week 12 | 11% | 48% | 7.4 (4.1, 13.4)
Week 52 | 16% | 57% | 7.4 (4.3, 12.6)

Table 13: Components of the ASDAS-MI and ASAS response criteria and other measures of disease activity in nr-axSpA patients at baseline, and at Week 12 in study nr-axSpA-1
 | Placebo |  | CIMZIA [CIMZIA administered every 2 weeks preceded by a loading dose of 400 mg at Weeks 0, 2, and 4] 200 mg every 2 weeks
 | N=158 |  | N=159
 | Baseline (SD) | Week 12 (SD) | Baseline (SD) | Week 12 (SD)
Total Spinal Pain (0-10) | 6.9 (1.8) | 6.0 (2.3) | 7.0 (1.9) | 3.9 (2.6)
Patient Global Assessment of Disease Activity (0-10) | 6.7 (2.0) | 5.9 (2.4) | 6.8 (1.9) | 3.8 (2.6)
C-Reactive Protein (mg/L) | 15.8 (17.7) | 13.2 (17.2) | 15.8 (17.8) | 6.7 (15.1)
BASDAI (0-10) [(BASDAI is Bath Ankylosing Spondylitis Disease Activity Index] | 6.8 (1.3) | 5.7 (2.1) | 6.9 (1.4) | 3.9 (2.2)
- Back Pain | 7.4 (1.3) | 6.2 (2.1) | 7.4 (1.4) | 4.1 (2.5)
- Peripheral pain and swelling (0-10) | 6.2 (2.2) | 5.3 (2.5) | 6.3 (2.3) | 3.7 (2.4)
- Inflammation [The average of BASDAI question 5 and 6 concerning morning stiffness intensity and duration.] | 6.7 (1.8) | 5.5 (2.4) | 6.9 (1.8) | 3.6 (2.4)
BASFI (0-10) [BASFI is Bath Ankylosing Spondylitis Functional Index] | 5.4 (2.2) | 4.9 (2.4) | 5.4 (2.1) | 3.2 (2.3)
BASMI [BASMI is Bath Ankylosing Spondylitis Metrology Index] | 2.8 (1.4) | 2.7 (1.4) | 3.0 (1.3) | 2.6 (1.4)
Mean and standard deviation in parenthesis were presented based on full analysis set.

The percentage of nr-axSpA patients achieving ASDAS-MI response by visit for study nr-axSpA-1 is shown in Figure 4.

Figure 4: Study nr-axSpA-1: ASDAS-MI response over 12 weeks [The same patients may not have responded at each time point.]

In study AS-1, at Week 12, patients with nr-axSpA treated with CIMZIA 200 mg every 2 weeks and CIMZIA 400 mg every 4 weeks had an ASAS 20 response of 42% and 47%, respectively, compared to 20% of patients treated with placebo. The ASAS 40 response in patients treated with CIMZIA 200 mg every 2 weeks and 400 mg every 4 weeks was 30% and 37%, respectively, compared to 11% of patients treated with placebo at Week 12 (see Section 14.4).

Other Health Related Outcomes

In study nr-axSpA-1, at Week 12, patients treated with CIMZIA achieved significantly greater improvement from baseline in the Ankylosing Spondylitis Quality of Life Questionnaire (ASQoL) score compared to patients treated with placebo.

14.7 Plaque Psoriasis

Three multicenter, randomized, double-blind studies (Study PS-1 [NCT02326298], Study PS-2 [NCT02326272], and Study PS-3 [NCT02346240]) enrolled subjects 18 years of age or older with moderate-to-severe plaque psoriasis who were eligible for systemic therapy or phototherapy. Subjects had a Physician Global Assessment (PGA) of ≥ 3 ("moderate") on a 5-category scale of overall disease severity, a Psoriasis Area and Severity Index (PASI) score ≥ 12, and body surface area (BSA) involvement of ≥ 10%.

Studies PS-1 (234 subjects) and PS-2 (227 subjects) randomized subjects to placebo, CIMZIA 200 mg every other week (following a loading dose of CIMZIA 400 mg at Weeks 0, 2, and 4), or CIMZIA 400 mg every other week. Studies PS-1 and PS-2 assessed the co-primary endpoints of the proportion of patients who achieved a PASI 75 and PGA of "clear" or "almost clear" with at least a 2-point improvement at Week 16. Other evaluated outcomes were PASI 90 at Week 16 and maintenance of efficacy to Week 48.

Study PS-3 randomized 559 subjects to receive placebo, CIMZIA 200 mg every other week (following a loading dose of CIMZIA 400 mg at Weeks 0, 2, and 4), CIMZIA 400 mg every other week up to Week 16, or a biologic comparator (up to Week 12). Study PS-3 assessed the proportion of patients who achieved a PASI 75 at Week 12 as the primary endpoint. Other evaluated outcomes were PGA of "clear" or "almost clear" at Week 16, PASI 75 at Week 16, PASI 90 at Week 16, and maintenance of efficacy to Week 48.

Of the 850 subjects randomized to receive placebo or CIMZIA in these placebo-controlled studies, 29% of patients were naïve to prior systemic therapy for the treatment of psoriasis, 47% had received prior phototherapy or chemophototherapy, and 30% had received prior biologic therapy for the treatment of psoriasis. Of the 850 subjects, 14% had received at least one TNF alpha agent and 16% had received an anti-IL agent. Eighteen percent of subjects reported a history of psoriatic arthritis at baseline.

Across all studies and treatment groups, the mean PASI score at baseline was 20 and ranged from 12 to 69. The baseline PGA score ranged from moderate (70%) to severe (30%). Mean baseline BSA was 25% and ranged from 10% to 96%. Subjects were predominantly men (64%) and White (94%), with a mean age of 46 years.

Clinical Response

Table 15 presents the efficacy results of PS-1, PS-2, and PS-3 at Week 16.

Table 15: Efficacy Results at Week 16 in Adults with Plaque Psoriasis in PS-1, PS-2, and PS-3 [MI [Missing data was imputed using multiple imputation based on the MCMC method.] ]
 | Study PS-1 |  |  | Study PS-2 |  |  | Study PS-3 [The primary endpoint in PS-3 was PASI 75 at Week 12.]
 | Placebo (N=51) | CIMZIA 200mg [Subjects received 400 mg of CIMZIA at Weeks 0, 2, and 4, followed by 200 mg every other week.] Q2W (N=95) | CIMZIA 400mg Q2W (N=88) | Placebo (N=49) | CIMZIA 200mg Q2W (N=91) | CIMZIA 400mg Q2W (N=87) | Placebo (N=57) | CIMZIA 200mg Q2W (N=165) | CIMZIA 400mg Q2W (N=167)
PGA of 0 or 1 [The co-primary efficacy endpoints at Week 16 in PS-1 and PS-2.] , [PGA score of 0 (clear) or 1 (almost clear).] | 4% | 45% | 55% | 3% | 61% | 65% | 4% | 52% | 62%
PASI 75 | 7% | 65% | 75% | 13% | 81% | 82% | 4% | 69% | 75%
PASI 90 | 0% | 36% | 44% | 5% | 50% | 52% | 0% | 40% | 49%

Examination of age, sex, prior use of biologics, and prior use of systemic therapies did not identify difference in response to CIMZIA among these subgroups.

Based on a post-hoc subgroup analysis in subjects with moderate-to-severe psoriasis, stratified by ≤90 kg or >90 kg, subjects with both lower body weight and lower disease severity may achieve an acceptable response with CIMZIA 200 mg.

Maintenance of Response

In PS-1 and PS-2, among subjects who were PASI 75 responders at Week 16 and received CIMZIA 400 mg every other week, the PASI 75 response rates at Week 48 were 94% and 81%, respectively. In subjects who were PASI 75 responders at Week 16 and received CIMZIA 200 mg every other week, the PASI 75 response rates at Week 48 were 81% and 74%, respectively.

In PS-1 and PS-2, among subjects who were PGA clear or almost clear responders at Week 16 and received CIMZIA 400 mg every other week, the PGA response rates at Week 48 were 79% and 73%, respectively. In subjects who were PGA clear or almost clear responders at Week 16 and received CIMZIA 200 mg every other week, the PGA response rates at Week 48 were 79% and 76%, respectively.

In PS-3 study, subjects who achieved a PASI 75 response at Week 16 were re-randomized to either continue treatment with CIMZIA or be withdrawn from therapy (i.e., receive placebo). At Week 48, 98% of subjects who continued on CIMZIA 400 mg every other week were PASI 75 responders as compared to 36% of subjects who were re-randomized to placebo. Among PASI 75 responders at Week 16 who received CIMZIA 200 mg every other week and were re-randomized to either CIMZIA 200 mg every other week or placebo, there was also a higher percentage of PASI 75 responders at Week 48 in the CIMZIA group as compared to placebo (80% and 46%, respectively).

16 HOW SUPPLIED/STORAGE AND HANDLING

How Supplied

CIMZIA (certolizumab pegol) for injection is a sterile white, lyophilized powder for subcutaneous use after reconstitution in the following packaging configuration.

Package size | NDC | Pack Contents
Carton of two 200 mg vials | NDC 50474-700-62 | Two 200 mg/vial glass vials with rubber stopper Two 1 mL Sterile Water for Injection, USP glass vials Two 3 mL plastic syringes Four 20-gauge needles (1 inch) Two 23-gauge needles (1 inch) Eight alcohol swabs

CIMZIA (certolizumab pegol) injection is a sterile, clear to opalescent, colorless to yellow solution for subcutaneous use in the following packaging configurations.

Package size | NDC | Pack Contents
Prefilled Syringe Starter Kit: each unit carton contains three cartons of two 200 mg/mL prefilled syringes per individual carton | NDC 50474-710-81 | Six 200 mg/mL prefilled syringes with a fixed 25 ½ gauge thin-wall needle 6 alcohol swabs
Carton of two 200 mg/mL prefilled syringes | NDC 50474-710-79 | Two 200 mg/mL prefilled syringe with a fixed 25 ½ gauge thin-wall needle Two alcohol swabs
Carton of one 200 mg/mL prefilled syringe | NDC 50474-750-10 | One 200 mg/mL prefilled syringe with a fixed 25 ½ gauge thin-wall needle One alcohol swab

The needle shield inside the removable cap of the CIMZIA prefilled syringe contains a derivative of natural rubber latex which may cause allergic reactions and should be handled with caution by latex-sensitive individuals [see Warnings and Precautions (5.4)].

Storage and Handling

Refrigerate CIMZIA vials and prefilled syringes between 2°C to 8°C (36°F to 46°F) in the original carton to protect from light. Do not freeze. Do not shake. Do not separate contents of carton prior to use. Do not use beyond expiration date, which is located on the drug label and carton.

Unopened CIMZIA lyophilized vials may also be stored at room temperature up to a maximum of 25°C (77°F) for 6 months, but not exceeding the original expiration date. If stored at room temperature, do not place back in refrigerator and write the new expiration date on the carton in the space provided.

When necessary, CIMZIA prefilled syringes may be stored at room temperature up to 77 °F (25 °C) in the original carton to protect from light for a single period of up to 7 days. Once stored at room temperature, do not place back in refrigerator. Write the date removed from the refrigerator in the space provided on the carton and discard if not used within the 7-day period.

17 PATIENT COUNSELING INFORMATION

Advise the patient and/or caregiver to read the FDA-approved patient labeling (Medication Guide and Instructions for Use)

Risk of Serious Infections

Inform patients that CIMZIA may lower the ability of the immune system to fight infections. Instruct patients of the importance of contacting their doctor if they develop any symptoms of infection, including tuberculosis and reactivation of hepatitis B virus infections.

Because caution should be exercised in prescribing CIMZIA to patients with clinically important active infections, advise patients of the importance of informing their health care providers about all aspects of their health [see Warnings and Precautions (5.1, 5.5)] .

Malignancies

Counsel patients about the possible risk of lymphoma and other malignancies while receiving CIMZIA [see Warnings and Precautions (5.2)] .

Other Medical Conditions

Advise patients to report any signs of new or worsening medical conditions such as heart disease, neurological disease, or autoimmune disorders [see Warnings and Precautions (5.3, 5.6, 5.9). Advise patients to report promptly any symptoms suggestive of a cytopenia such as bruising, bleeding, or persistent fever [see Warnings and Precautions (5.7)] .

Hypersensitivity Reactions

Advise patients to seek immediate medical attention if they experience any symptoms of severe hypersensitivity reactions. Advise latex-sensitive patients that the needle shield inside the removable cap of the CIMZIA prefilled syringe contains a derivative of natural rubber latex [see Warnings and Precautions (5.4)] .

Preparation and Administration of CIMZIA Using the Prefilled Syringe

Instruct patients and caregivers on how to inject the Prefilled Syringe. Complete instructions are provided in the Instructions for Usepackaged in each CIMZIA Prefilled Syringe kit.

- If refrigerated, remove the prefilled syringe from the carton and let it warm to room temperature.
- Inspect the liquid in the prefilled syringe. It should be clear to opalescent, and colorless to yellow and free from particulates. Discard the syringe if cloudy, discolored or contains particulates.
- Suitable sites for injection include the thigh or abdomen. Inject at least 1 inch from the previous site.
- Do not inject into areas where the skin is tender, bruised, red or hard, or where there are scars or stretch marks.

Instruct patients and caregivers in proper syringe and needle disposal technique.

- To avoid needle-stick injury, do not to place the needle cap back on the syringe or otherwise recap the needle.
- Properly dispose of needles and syringes in a puncture-proof container.
- Do not reuse the injection materials.

Manufactured by:
UCB, Inc.
1950 Lake Park Drive
Smyrna, GA 30080

US License No. 1736

MEDICATION GUIDE
CIMZIA®(CIM-zee-uh)
(certolizumab pegol)
injection for subcutaneous use

What is the most important information I should know about CIMZIA?
CIMZIA may cause serious side effects, including:

- CIMZIA is a prescription medicine called a Tumor Necrosis Factor (TNF) blockerthat can lower the ability of your immune system to fight infections. Some people who received CIMZIA have developed serious infections, including tuberculosis (TB) and infections caused by viruses, fungi, or bacteria that have spread throughout the body. Some of these serious infections have caused hospitalization and death.
  - Your healthcare provider should test you for TB before starting CIMZIA.
  - Your healthcare provider should monitor you closely for signs and symptoms of TB during treatment with CIMZIA.
  Before starting CIMZIA, tell your healthcare provider if you:
  - think you have an infection or have symptoms of an infection such as:

- fever, sweat, or chills
- cough
- blood in phlegm
- warm, red, or painful skin or sores on your body
- burning when you urinate or urinate more often than normal

- muscle aches
- shortness of breath
- weight loss
- diarrhea or stomach pain
- feeling very tired

- are being treated for an infection.
- get a lot of infections or have infections that keep coming back.
- have diabetes, HIV-1 or a weak immune system. People with these conditions have a higher chance for infections.
- have tuberculosis (TB), or have been in close contact with someone with TB.
- were born in, live, have lived, or traveled to certain countries where there is more risk for getting TB. Ask your healthcare provider if you are not sure.
- live, have lived, or traveled to certain parts of the country (such as the Ohio and Mississippi River valleys and the Southwest) where there is an increased risk for getting certain kinds of fungal infections (histoplasmosis, coccidioidomycosis, candidiasis, aspergillosis, blastomycosis, and pneumocystosis). These infections may develop or become more severe if you receive CIMZIA. Ask your healthcare provider if you do not know if you have lived in an area where these infections are common.
- have or have had hepatitis B.
- use the medicine Kineret (anakinra), Orencia®(abatacept), Rituxan®(rituximab), or Tysabri®(natalizumab).

Stop using CIMZIA, and tell your healthcare provider right awayif you have any of the symptoms of an infection listed above.

- Cancer.
  - For people who receive TNF blockers, including CIMZIA, the chances of getting certain types of cancers may increase.
  - Some children, teenagers, and young adults who received TNF blockers, including CIMZIA, have developed lymphoma and other certain types of rare cancers, some of which have caused death. These cancers are not usually seen in this age group.
  - People with inflammatory diseases including rheumatoid arthritis, psoriatic arthritis, or ankylosing spondylitis, especially those with very active disease, may be more likely to get lymphoma.
  - Some people who receive TNF blockers, including CIMZIA, have developed a rare type of cancer which may cause death, called hepatosplenic T-cell lymphoma. Most of these people were male teenagers and young adult males with Crohn's disease or ulcerative colitis. Also, most of these people had been treated with both a TNF blocker and another medicine called IMURAN®(azathioprine) or PURINETHOL®(6-mercaptopurine, 6-MP).
  - Some people who receive CIMZIA, have developed certain types of skin cancer. Tell your healthcare provider if you develop any changes in the appearance of your skin, including growths on your skin, during or after treatment with CIMZIA. You should see your healthcare provider periodically during treatment for skin examinations, especially if you have a history of skin cancer.

What is CIMZIA?
CIMZIA is a prescription medicine called a Tumor Necrosis Factor (TNF) blocker used to:

- Lessen the signs and symptoms of moderately to severely active Crohn's disease (CD) in adults who have not been helped enough by usual treatments
- Treat moderately to severely active rheumatoid arthritis (RA) in adults
- Treat active polyarticular juvenile idiopathic arthritis (pJIA) in patients 2 years of age and older
- Treat active psoriatic arthritis (PsA) in adults
- Treat active ankylosing spondylitis (AS) in adults
- Treat active non-radiographic axial spondyloarthritis (nr-axSpA) with measures of inflammation in adults
- Treat moderate to severe plaque psoriasis (PsO) in adults who may benefit from taking injections or pills (systemic therapy) or phototherapy (treatment using ultraviolet light alone or with pills)

Before receiving CIMZIA, tell your healthcare provider about all of your medical conditions, including if you:

- have an infection.
- have or have had lymphoma or any other type of cancer.
- have or had congestive heart failure.
- are allergic to rubber or latex. The plastic needle shield inside the removable cap of the prefilled syringe contains natural rubber.
- have or have had seizures, any numbness or tingling, or a disease that affects your nervous system such as multiple sclerosis or Guillain-Barre syndrome.
- have or had serious blood conditions.
- are scheduled to receive a vaccine. Do not receive a live vaccine immediately before starting treatment with CIMZIA or while receiving CIMZIA.
- are allergic to certolizumab pegol or any of the ingredients in CIMZIA. See the end of this Medication Guide for a complete list of the ingredients in CIMZIA.
- are pregnant or plan to become pregnant. You and your doctor should decide if you should continue to take CIMZIA while you are pregnant. It is not known if CIMZIA will harm your unborn baby.
- are breastfeeding or plan to breastfeed. Talk to your healthcare provider about the best way to feed your baby during treatment with CIMZIA.

Tell your healthcare provider about all the medicines you take, including prescription and over-the-counter medicines, vitamins, and herbal supplements.
Know the medicines you take. Keep a list of them to show to your healthcare provider and pharmacist when you get a new medicine.

How will I receive CIMZIA?

- CIMZIA comes as lyophilized powder or as a solution in a prefilled syringe for injection.
  - If your healthcare provider prescribes the CIMZIA powder, it should be injected by a healthcare provider. Each dose of CIMZIA will be given as 1 or 2 separate injections under the skin (subcutaneous injection) in your stomach area (abdomen) or upper thighs.
  - If your healthcare provider prescribes the CIMZIA prefilled syringe, you will be trained on how to inject CIMZIA.
- You will receive a CIMZIA Prefilled Syringe Kitincluding a complete Instructions for Usebooklet for instructions on how to inject CIMZIA the right way.
- Read the detailed Instructions for Use for instructions about how to prepare and inject your dose of CIMZIA, and how to properly throw away used syringes containing the needle.
- Do not give yourself an injection of CIMZIA unless you have been shown by your healthcare provider. A family member or friend can also be trained to help you give your injection. Talk to your healthcare provider if you have questions.
- CIMZIA prefilled syringe is given as an injection under the skin (subcutaneous injection) in your stomach area (abdomen) or upper thighs. Your healthcare provider will tell you how much and how often to inject CIMZIA. Do not use more CIMZIA or inject more often than prescribed.
- You may need more than 1 injection at a time depending on your prescribed dose of CIMZIA. If you are prescribed more than 1 injection, each injection should be given at a different site in your stomach or upper thighs and at least 1 inch from your last injection.
- Make sure the solution in the CIMZIA prefilled syringe is clear to opalescent, and colorless to yellow and free from particles. Do not use the CIMZIA prefilled syringe if the medicine is cloudy, discolored, or contains particles.

What are the possible side effects of CIMZIA?
CIMZIA can cause serious side effects, including:

- See " What is the most important information I should know about CIMZIA?"
- Heart failure including new heart failure or worsening of heart failure you already have.Symptoms include shortness of breath, swelling of your ankles or feet, or sudden weight gain.
- Allergic reactions.Get medical help right away if you have any signs of an allergic reaction which include a skin rash, swelling or itching of the face, tongue, lips, or throat, or trouble breathing.
  The plastic needle shield inside the removable cap of the prefilled syringe contains natural rubber and may cause an allergic reaction if you are sensitive to latex.
- Hepatitis B virus reactivation in people who carry the virus in their blood.In some cases, people who received CIMZIA have died because of the hepatitis B virus being reactivated. Your healthcare provider should monitor you carefully before and during treatment with CIMZIA to see if you carry the hepatitis B virus in your blood. Tell your healthcare provider if you have any of the following symptoms:

- feel unwell
- tiredness (fatigue)
- pain on the right side of your stomach (abdomen)

- skin or eyes look yellow
- poor appetite or vomiting

- New or worsening nervous system problems, such as multiple sclerosis (MS), Guillain-Barre syndrome, seizures, or inflammation of the nerves of the eyes.Symptoms may include:

- dizziness
- problems with your vision

- numbness or tingling
- weakness in your arms or legs

- Blood problems.Your body may not make enough of the blood cells that help fight infections or help stop bleeding. Symptoms include a fever that does not go away, bruising or bleeding very easily, or looking very pale. Tell your healthcare provider right away if you have any bruising, bleeding or a fever that does not go away.
- Immune reactions including a lupus-like syndrome.Symptoms include shortness of breath, joint pain, or a rash on the cheeks or arms that worsens with sun exposure.

Call your healthcare provider right away if you have any serious side effects listed above.
The most common side effects of CIMZIA includeupper respiratory infections (flu, cold), rash, urinary tract infections (bladder infections).
These are not all of the possible side effects of CIMZIA.
Call your doctor for medical advice about side effects. You may report side effects to FDA at 1-800-FDA-1088.

How should I store CIMZIA?

- Keep CIMZIA in the refrigerator between 36°F to 46°F (2°C to 8°C).
- Do not freeze CIMZIA. Do not shake.
- Protect CIMZIA from light .Store CIMZIA in the carton it came in.
- Do not use CIMZIA if the medicine is expired. Check the expiration date on the prefilled syringe or carton.
- If needed, CIMZIA syringes may be stored at room temperature up to 77ºF (25ºC) in the original carton to protect from light for a single period of up to 7 days. After your CIMZIA syringe has been stored at room temperature, do not place back in refrigerator.
- Write the date removed from the refrigerator in the space provided on the carton and throw away (discard) if not used within the 7-day period.
- The CIMZIA prefilled syringe is made of glass. Do not drop or crush the syringe.

Keep CIMZIA and all medicines out of the reach of children.

General information about the safe and effective use of CIMZIA.
Medicines are sometimes prescribed for purposes other than those listed in a Medication Guide. Do not use CIMZIA for a condition for which it was not prescribed. Do not give CIMZIA to other people, even if they have the same symptoms that you have. It may harm them. You can ask your pharmacist or healthcare provider for information about CIMZIA that is written for health professionals.

What are the ingredients in CIMZIA?
CIMZIA lyophilized powder:
Active ingredient: certolizumab pegol
Inactive ingredients:lactic acid, polysorbate, sucrose
CIMZIA lyophilized powder is mixed with sterile Water for Injection.
CIMZIA prefilled syringe:
Active ingredient: certolizumab pegol
Inactive ingredients:sodium acetate, sodium chloride, Water for Injection
CIMZIA has no preservatives.
Product manufactured by:
UCB, Inc. 1950 Lake Park Drive Smyrna, GA 30080
US License No. 1736
For more information, go to www.CIMZIA.com or call 1-866-424-6942.

This Medication Guide has been approved by the U.S. Food and Drug Administration.

Revised: 09/2025

Instructions for Use

CIMZIA®(CIM-zee-uh)
(certolizumab pegol)
injection for subcutaneous use
Prefilled Syringes

Read this Instructions for Use booklet that comes with CIMZIA before you start receiving it, and before each injection of CIMZIA. This Instructions for Use booklet does not take the place of talking with your healthcare provider about your medical condition or treatment. These instructions are for 1 injection only. You may need more than 1 injection at a time depending on your prescribed dose of CIMZIA.

Do not share your CIMZIA Prefilled Syringe with needle attached with another person. You may give another person an infection or get an infection from them.
Important: The plastic needle shield inside the removable cap contains natural rubber. Tell your healthcare provider if you are allergic to latex.
Supplies you will need to give your CIMZIA injection: See Figure Aand Figure B.

- 1 CIMZIA prefilled syringe with needle attached. You may need 2 CIMZIA prefilled syringes with needles attached to give higher doses.
- 1 or 2 alcohol swabs
- 1 or 2 clean cotton balls or gauze pads
- 1 puncture-resistant sharps disposal container. See " Disposal of your syringes with needles attached" at the end of this Instructions for Use booklet.

CIMZIA comes in a tray containing either 1 or 2 prefilled glass syringes. Use a new CIMZIA syringe for each injection.

Storage information:

- Keep CIMZIA in the refrigerator between 36°F to 46°F (2°C to 8°C).
- Do not freeze. Do not shake.
- Protect CIMZIA from light. Store CIMZIA in the carton it came in.
- Do not use CIMZIA if the medicine is expired. Check the expiration date on the prefilled syringe or carton.
- If needed, CIMZIA syringes may be stored at room temperature up to 77°F (25°C) in the original carton to protect from light for a single period of up to 7 days. After your CIMZIA syringe has been stored at room temperature, do not place back in refrigerator.
- Write the date removed from the refrigerator in the space provided on the carton and throw away (discard) if not used within the 7-day period.

Setting up for your CIMZIA injection:
Step 1.
If refrigerated, take the carton containing the number of prefilled syringes needed for your dosage of CIMZIA out of the refrigerator. Check the expiration date on the syringe carton and label. See Figure C.

If the expiration date has passed, do notuse the syringe. Call your pharmacist for questions about the expiration date. Do not use CIMZIA if the carton has been opened or tampered with.

Step 2.
Remove the prefilled syringe from the carton and let it warm to room temperature, this will take about 30 minutes. Do not warm the syringe in any other way. If you have a second syringe and are not using the syringe, put the carton containing the remaining prefilled syringe back in the refrigerator.

Step 3.
Find a clean, flat work surface, such as a table.

Step 4.
Make sure the liquid medicine in the prefilled syringe is clear to opalescent, and colorless to yellow and free from particles. Do notinject the medicine if it is cloudy, discolored, or contains particles. Call your healthcare provider or pharmacist if you have any questions about your CIMZIA prefilled syringe.

Step 5.
Gather all the supplies you will need for your injection.

Step 6.
Wash your hands with soap and warm water and dry with a clean towel.

Selecting and preparing your injection site:

Step 7.
Choose your injection sites on your stomach or upper thighs. See Figure D.

- Choose a new injection site each time you use CIMZIA.
- Each new injection should be given at least 1 inch from the site you used before. If you choose your stomach, avoid the 2 inches around your belly button (navel).
- Do not inject into areas where your skin is tender, bruised, red or hard, or where you have scars or stretch marks.
- Change injection sites between your stomach and upper thighs to reduce the chance of having a skin reaction.
- You may want to write down the site you use for your injection to help you remember to use a different site each time you inject.

Step 8.
Clean your injection site with an alcohol swab. Let the area dry completely.

Giving your CIMZIA injection:
Step 9.
Pick up the prefilled syringe with 1 hand and hold it with the needle pointing up. You may see air bubbles. This is normal. There is no need to remove air bubbles before giving your injection. Injecting the solution with air bubbles will not harm you. With your other hand, remove the plastic ring needle cap by pulling straight up on the plastic ring. See Figure E.

Do nottouch the needle and do not let the needle touch any surface.
Do not bend the needle. Place the plastic ring needle cap to the side.

Step 10.
With your other hand, gently pinch a fold of skin at the cleaned injection site. See Figure F.

Step 11.
With a quick, dart-like motion, insert the needle into your skin at about a 45-degree angle. Release the pinched skin, keeping the syringe in position. Slowly push on the plunger all the way down until the syringe is empty. See Figure G.

Step 12.
When the syringe is empty, pull the needle out of your skin while carefully keeping the needle at the same angle as inserted. See Figure H.

Step 13.
Place a dry cotton ball or gauze pad over the injection site for several seconds. See Figure I.

Do not rub the injection site. Do not use an alcohol swab as it may cause stinging. If there is a little bleeding, cover the injection site with a small bandage.
To avoid a needle-stick injury, do not try to recap the needle.
Do not reuse any of your injection supplies.

Disposal of your syringes with needles attached:
Put your used syringes with needle attached in a FDA-cleared sharps disposal container right away after use. See Figure J.

Do not throw away (dispose of) loose syringes and needles in your household trash.

- If you do not have a FDA-cleared sharps disposal container, you may use a household container that is:
  - made of a heavy-duty plastic
  - can be closed with a tight-fitting, puncture-resistant lid, without sharps being able to come out
  - upright and stable during use
  - leak-resistant
  - properly labeled to warn of hazardous waste inside the container
    - When your sharps disposal container is almost full, you will need to follow your community guidelines for the right way to dispose of your sharps disposal container. There may be state or local laws about how you should throw away used needles and syringes. For more information about safe sharps disposal, and for specific information about sharps disposal in the state that you live in, go to the FDA's website at: http://www.fda.gov/safesharpsdisposal.

Do not dispose of your used sharps disposal container in your household trash unless your community guidelines permit this. Do not recycle your used sharps disposal container.

This Instructions for Use has been approved by the U.S. Food and Drug Administration.

Product manufactured by:
UCB, Inc.
1950 Lake Park Drive
Smyrna, GA 30080

Revised: 9/2024

INSTRUCTIONS FOR USE

CIMZIA®
(certolizumab pegol)

Preparation and Administration of Lyophilized
Powder for Injection
(200 mg/vial)

CIMZIA Lyophilized powder should be prepared and administered by a health care professional.

Contents:
2 inner kits, each containing 1 vial of CIMZIA 200 mg, 1 vial of sterile water for injection (USP 1 mL), 1 single-dose plastic syringe, 4 alcohol swabs, two reconstitution needles, and one dosing needle.

Refrigerate carton at 2 to 8°C (36 to 46°F). DO NOT FREEZE. Do not separate contents of carton prior to use. Do not use beyond expiration date on container.

Unopened CIMZIA vials may also be stored at room temperature up to a maximum of 25°C (77°F) for 6 months, but not exceeding the original expiration date. If stored at room temperature, do not place back in refrigerator and write the new expiration date on the carton in the space provided.

If refrigerated, remove CIMZIA from the refrigerator and allow the vial(s) to sit at room temperature for 30 minutes before reconstituting. Do not warm the vial in any other way. Using appropriate aseptic technique, reconstitute each lyophilized vial of CIMZIA with 1 mL of sterile water for injection using a syringe with a fresh 20-gauge needle. The sterile water for injection should be directed at the vial wall rather than directly on CIMZIA. (See Figure 1.)

The resultant solution will contain 200 mg/mL.

Gently swirl each vial of CIMZIA for about one minute without shaking, ensuring that all of the powder comes into contact with the Sterile Water for Injection. The swirling should be as gentle as possible in order to avoid creating a foaming effect. (See Figure 2.)

Continue swirling every 5 minutes as long as non-dissolved particles are observed. Full reconstitution may take as long as 30 minutes. The final reconstituted solution contains 200 mg/mL and should be clear to opalescent, colorless to yellow liquid and essentially free from particulates.

Once reconstituted, CIMZIA can be stored in the vials for up to 24 hours between 2° to 8° C (36° to 46° F) prior to injection. Do not freeze.

When ready to inject, reconstituted CIMZIA should be at room temperature. Do not leave reconstituted CIMZIA at room temperature for more than 2 hours prior to administration.

Withdraw the reconstituted solution into a separate syringe for each vial using a new 20-gauge needle for each vial so that each syringe contains the required volume of CIMZIA. (See Figure 3.)

Replace the 20-gauge needle(s) on the syringes with a 23-gauge needle(s) for administration. (See Figure 4.)

Inject the full contents of the syringe(s) subcutaneously by pinching the skin of the abdomen (See Figure 5) or thigh (See Figure 6). Where a 400 mg dose is required, two injections are required. Therefore, separate sites should be used for each 200 mg injection.

OR

You can also visit the CIMZIA Web site at www.cimziahcp.com

9/2024

U.S. License No. 1736
Manufactured by UCB Inc. Smyrna GA 30080
UCB Pharma S.A.

PRINCIPAL DISPLAY PANEL - Kit Carton

NDC 50474-700-62

Rx ONLY

OPEN HERE

cimzia®
(certolizumab pegol)

200 mg/vial

FOR SUBCUTANEOUS USE ONLY

Single-dose vial. Discard unused portion.

No US standard of potency

MUST BE RECONSTITUTED

Dispense the enclosed Medication Guide to each patient.

See package insert for reconstitution and dosage information.

After reconstitution with 1 mL of Sterile Water for Injection, USP, each mL
contains 200 mg of certolizumab pegol.

Storage
Refrigerate carton at 2° to 8° C (36° to 46° F) in carton to protect from
light. Do Not Freeze.

Unopened vials may be stored at room temperature up to a maximum of
25°C (77°F) for 6 months. If stored at room temperature, do not place back
in refrigerator and discard after:

___/___/___

Contains 2 vials of certolizumab pegol, each containing 200 mg

ucb

DO NOT SEPARATE CONTENTS
OF CARTON PRIOR TO USE

PRINCIPAL DISPLAY PANEL - 1 mL Syringe Carton - 50474-710-79

NDC 50474-710-79
Rx ONLY

Dispense the enclosed Medication Guide to each patient.

Contains 2 single-dose, prefilled syringes each containing
200 mg/mL of CIMZIA and 2 alcohol swabs.

cimzia®
(certolizumab pegol)

2 x 200 mg/mL
PREFILLED SYRINGES

FOR SUBCUTANEOUS INJECTION USE ONLY

LIFT HERE TO OPEN

Each syringe is intended for a single dose
and any remaining product in the syringe
should be discarded after a single use.

DO NOT FREEZE
DO NOT SHAKE

PRINCIPAL DISPLAY PANEL - 1 mL Syringe Carton Box

NDC 50474-710-81

Rx ONLY

Dispense the enclosed Medication Guide to each patient.

cimzia®
(certolizumab pegol)

STARTER KIT

3 cartons of 2 x 200 mg/mL
PREFILLED SYRINGES

FOR SUBCUTANEOUS INJECTION USE ONLY

The entire carton is to be dispensed as one unit.

Each unit carton contains three individual cartons (doses).
Each individual carton (dose) contains:
2 single-dose prefilled syringes (200 mg/1mL) and 2 alcohol swabs.

PRINCIPAL DISPLAY PANEL - 1 mL Syringe Carton - 50474-750-10

NDC 50474-750-10
Rx ONLY

cimzia®
(certolizumab pegol)
Injection

200 mg/vial

FOR SUBCUTANEOUS USE ONLY

Dispense the enclosed Medication Guide to each patient.

Contents: One single-dose prefilled syringe.
Discard unused portion.

One alcohol swab.